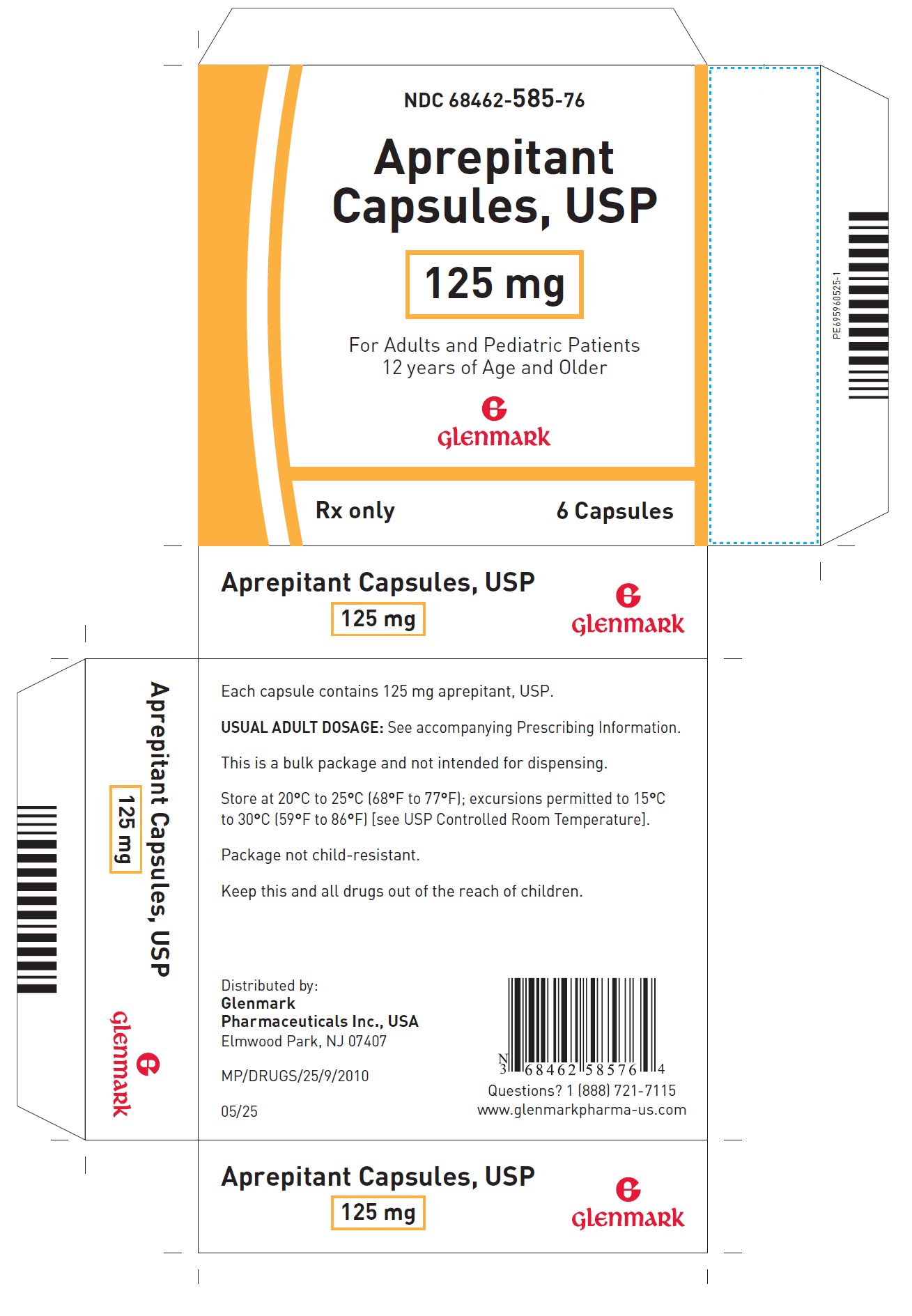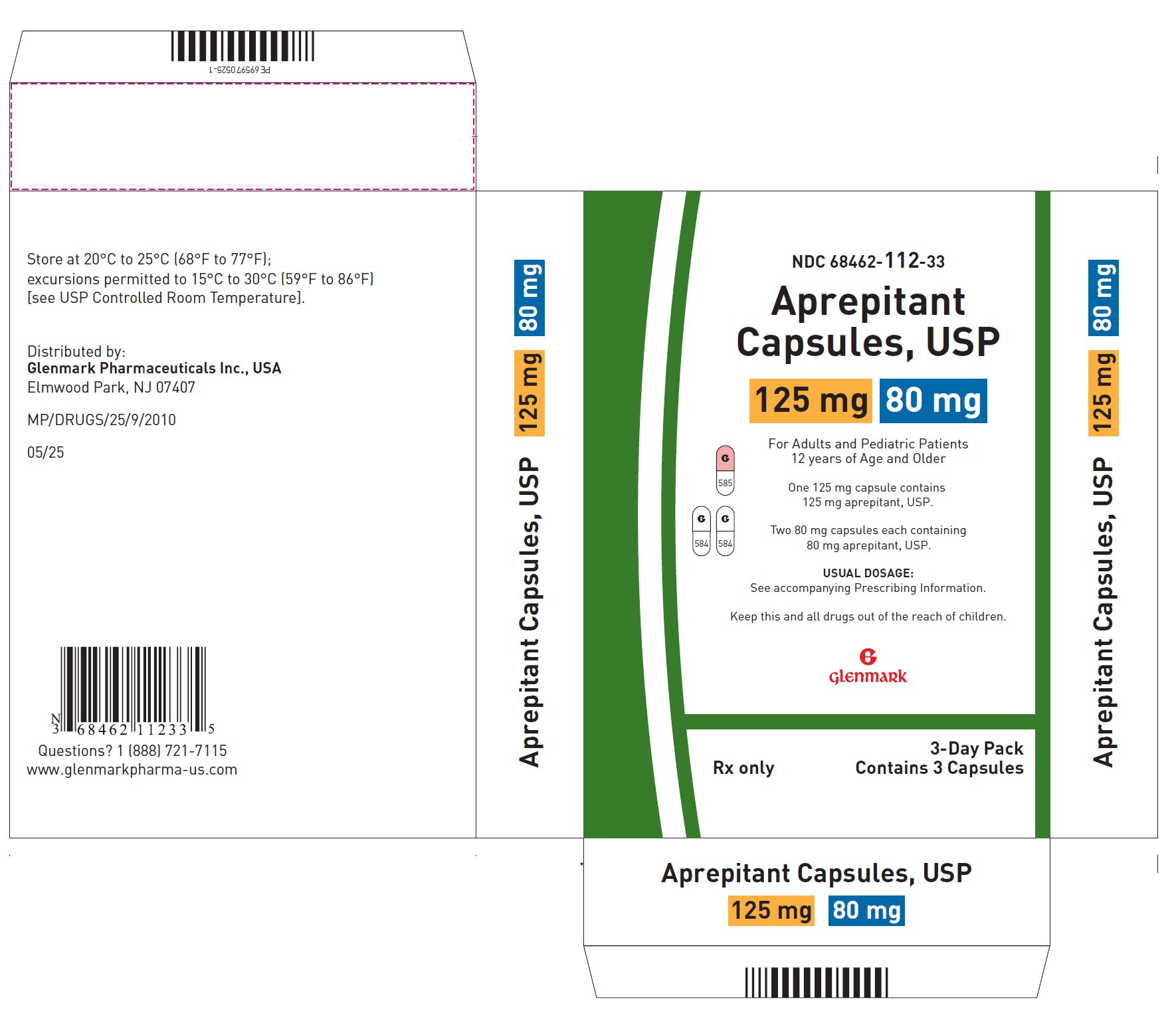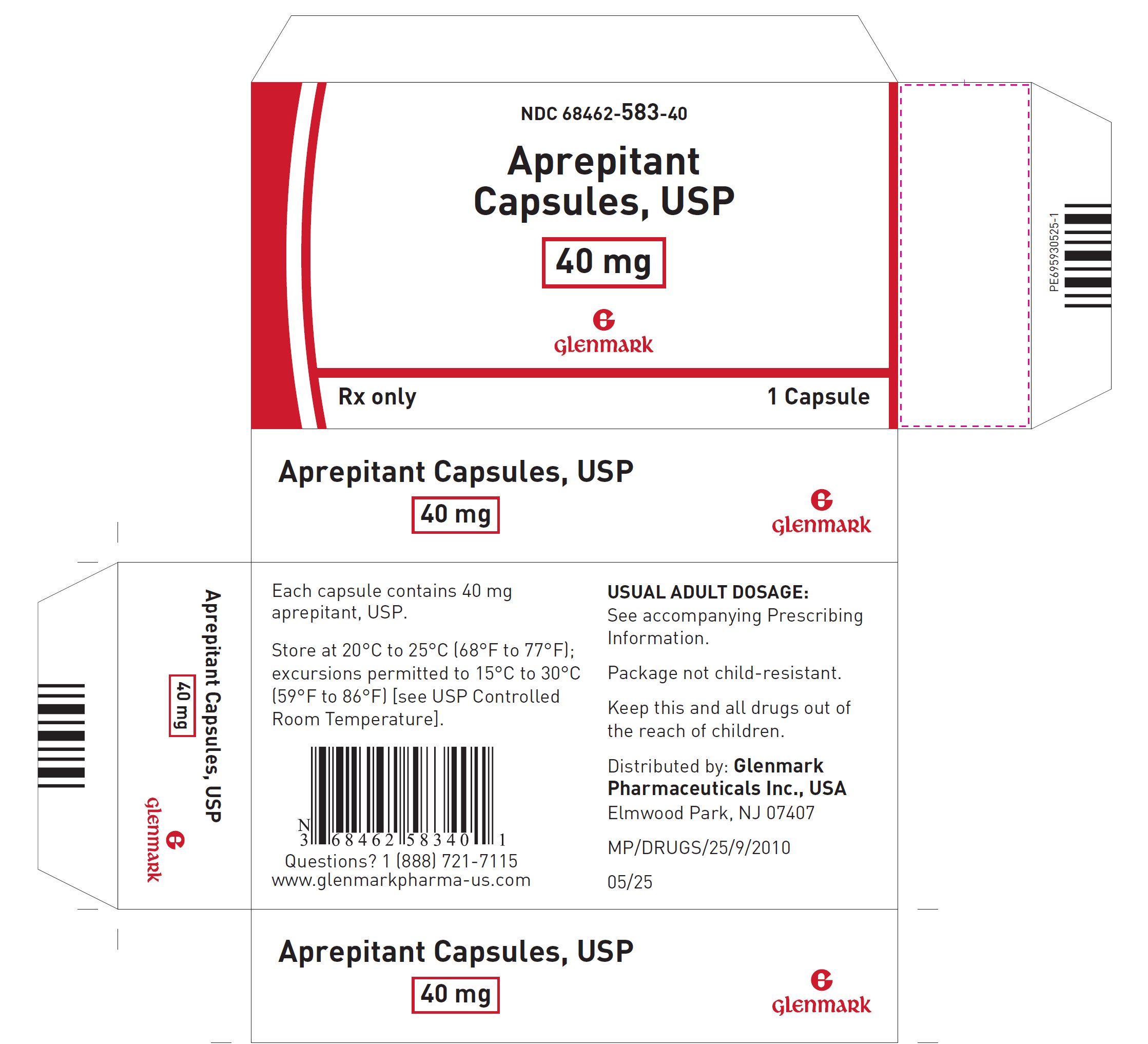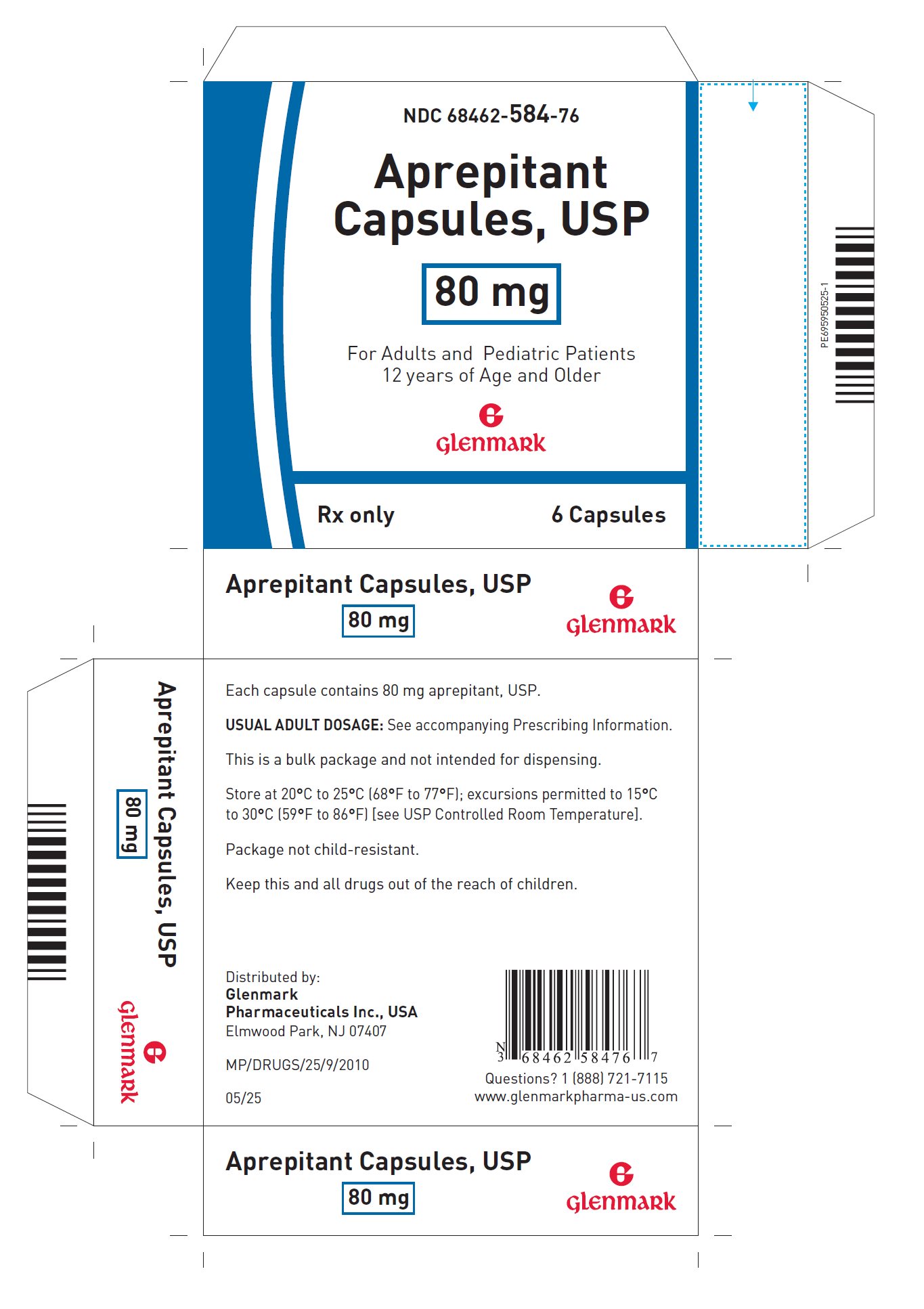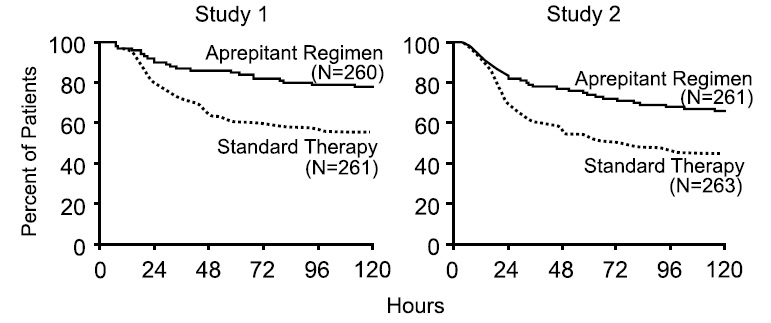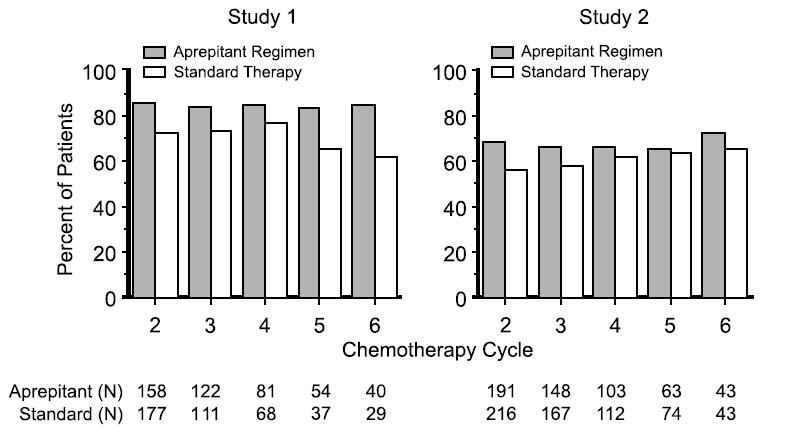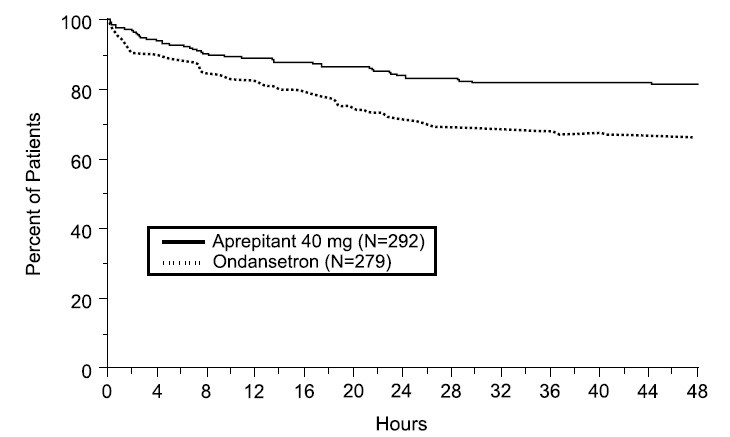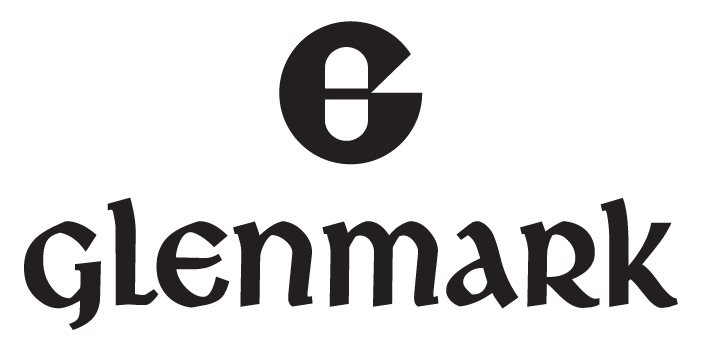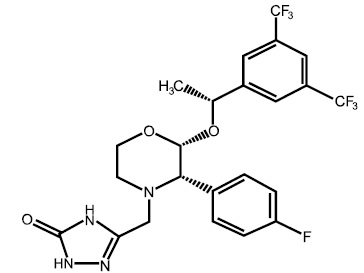 DRUG LABEL: Aprepitant
NDC: 68462-583 | Form: CAPSULE
Manufacturer: Glenmark Pharmaceuticals Inc., USA
Category: prescription | Type: HUMAN PRESCRIPTION DRUG LABEL
Date: 20260128

ACTIVE INGREDIENTS: APREPITANT 40 mg/1 1
INACTIVE INGREDIENTS: SILICON DIOXIDE; HYDROXYETHYL CELLULOSE (140 MPA.S AT 5%); MICROCRYSTALLINE CELLULOSE; MANNITOL; POLOXAMER 407; POVIDONE, UNSPECIFIED; SODIUM STEARYL FUMARATE; VITAMIN E POLYETHYLENE GLYCOL SUCCINATE; WATER; GELATIN, UNSPECIFIED; SODIUM LAURYL SULFATE; TITANIUM DIOXIDE; FERRIC OXIDE YELLOW; SHELLAC; FERROSOFERRIC OXIDE; POTASSIUM HYDROXIDE

HIGHLIGHTS OF PRESCRIBING INFORMATION

These highlights do not include all the information needed to use APREPITANT CAPSULES safely and effectively. See full prescribing information for APREPITANT CAPSULES.
APREPITANT capsules, for oral use
Initial U.S. Approval: 2003

1 INDICATIONS AND USAGE

Aprepitant is a substance P/neurokinin 1 (NK1) receptor antagonist.

Aprepitant capsules are indicated

- in combination with other antiemetic agents, in patients 12 years of age and older for prevention of:
- acute and delayed nausea and vomiting associated with initial and repeat courses of highly emetogenic cancer chemotherapy (HEC) including high-dose cisplatin (1.1)
  - nausea and vomiting associated with initial and repeat courses of moderately emetogenic cancer chemotherapy (MEC) (1.1)
- for prevention of postoperative nausea and vomiting (PONV) in adults (1.2)

Limitations of Use: (1.3)

- Aprepitant has not been studied for treatment of established nausea and vomiting.
- Chronic continuous administration of aprepitant is not recommended.

2 DOSAGE AND ADMINISTRATION

Prevention of Chemotherapy Induced Nausea and Vomiting (CINV) (2.1)

- Aprepitant capsules in adults and pediatric patients 12 years of age and older: is 125 mg on Day 1 and 80 mg on Days 2 and 3.
- Administer aprepitant 1 hour prior to chemotherapy on Days 1, 2, and 3. If no chemotherapy is given on Days 2 and 3, administer aprepitant in morning.
- See Full Prescribing Information for recommended dosages of concomitant dexamethasone and 5-HT3 antagonist for HEC and MEC.

Prevention of PONV (2.2)

- Adults: 40 mg aprepitant capsules within 3 hours prior to induction of anesthesia.

Administration (2.4)

- Aprepitant capsules can be administered with or without food.
- Swallow aprepitant capsules whole.

3 DOSAGE FORMS AND STRENGTHS

Aprepitant Capsules, USP: 40 mg; 80 mg; 125 mg (3)

4 CONTRAINDICATIONS

- Known hypersensitivity to any component of this drug. (4)
- Concurrent use with pimozide. (4)

5 WARNINGS AND PRECAUTIONS

- CYP3A4 Interactions: Aprepitant is a substrate, weak-to-moderate inhibitor and inducer of CYP3A4; See Full Prescribing Information for recommendations regarding contraindications, risk of adverse reactions, and dosage adjustments of aprepitant and concomitant drugs. (4, 5.1, 7.1, 7.2)
- Warfarin (a CYP2C9 substrate): Risk of decreased INR of prothrombin time; monitor INR in 2-week period, particularly at 7 to 10 days, following initiation of aprepitant. (5.2, 7.1)
- Hormonal Contraceptives: Efficacy of contraceptives may be reduced during administration of and for 28 days following the last dose of aprepitant. Use effective alternative or back-up methods of contraception. (5.3, 7.1, 8.3)

6 ADVERSE REACTIONS

Most common adverse reactions are (6.1):

Prevention of Chemotherapy Induced Nausea and Vomiting (CINV)

- Adults (≥3%): fatigue, diarrhea, asthenia, dyspepsia, abdominal pain, hiccups, white blood cell count decreased, dehydration, and alanine aminotransferase increased.
- Pediatrics (≥3%): neutropenia, headache, diarrhea, decreased appetite, cough, fatigue, hemoglobin decreased, dizziness, and hiccups.

PONV

- Adults (≥3%): constipation and hypotension.

To report SUSPECTED ADVERSE REACTIONS, contact Glenmark Pharmaceuticals Inc., USA at 1 (888) 721-7115 or FDA at 1-800-FDA-1088 or www.fda.gov/medwatch.

7 DRUG INTERACTIONS

See Full Prescribing Information for a list of clinically significant drug interactions. (4, 5.1, 5.2, 5.3, 7.1, 7.2)

FULL PRESCRIBING INFORMATION

1 INDICATIONS AND USAGE

1.1 Prevention of Chemotherapy Induced Nausea and Vomiting (CINV)

Aprepitant capsules, in combination with other antiemetic agents, are indicated in patients 12 years of age and older for the prevention of:

- acute and delayed nausea and vomiting associated with initial and repeat courses of highly emetogenic cancer chemotherapy (HEC) including high-dose cisplatin.
- nausea and vomiting associated with initial and repeat courses of moderately emetogenic cancer chemotherapy (MEC).

1.2 Prevention of Postoperative Nausea and Vomiting (PONV)

Aprepitant capsules are indicated in adults for the prevention of postoperative nausea and vomiting.

1.3 Limitations of Use

- Aprepitant has not been studied for the treatment of established nausea and vomiting.
- Chronic continuous administration of aprepitant is not recommended because it has not been studied, and because the drug interaction profile may change during chronic continuous use.

2 DOSAGE AND ADMINISTRATION

2.1 Prevention of Chemotherapy Induced Nausea and Vomiting (CINV)

Adults and Pediatric Patients 12 Years of Age and Older

The recommended oral dosage of aprepitant capsules, dexamethasone, and a 5-HT3 antagonist in adults and pediatric patients 12 years of age and older who can swallow oral capsules for the prevention of nausea and vomiting associated with administration of HEC or MEC is shown in Table 1 or Table 2, respectively.

Table 1: Recommended Dosing for the Prevention of Nausea and Vomiting Associated with HEC
 | Population | Day 1 | Day 2 | Day 3 | Day 4
Aprepitant capsules* | Adults and Pediatric Patients 12 Years and Older | 125 mg orally | 80 mg orally | 80 mg orally | none
Dexamethasone | Adults | 12 mg orally | 8 mg orally | 8 mg orally | 8 mg orally
Dexamethasone | Pediatric Patients 12 Years and Older | If a corticosteroid, such as dexamethasone, is co-administered, administer 50% of the recommended corticosteroid dose on Days 1 through 4 [see Clinical Studies (14.3)].
5-HT3 antagonist | Adults and Pediatric Patients 12 Years and Older | See selected 5-HT3 antagonist prescribing information for the recommended dosage | none | none | none

* Administer aprepitant capsules 1 hour prior to chemotherapy treatment on Days 1, 2, and 3. If no chemotherapy is given on Days 2 and 3, administer aprepitant capsules in the morning.

† Administer dexamethasone 30 minutes prior to chemotherapy treatment on Day 1 and in the morning on Days 2 through 4. A 50% dosage reduction of dexamethasone is recommended to account for a drug interaction with aprepitant [see Clinical Pharmacology (12.3)].

Table 2: Recommended Dosing for the Prevention of Nausea and Vomiting Associated with MEC
 | Population | Day 1 | Day 2 | Day 3
Aprepitant capsules* | Adults and Pediatric Patients 12 Years and Older | 125 mg orally | 80 mg orally | 80 mg orally
Dexamethasone | Adults | 12 mg orally | none | none
 | Pediatric Patients 12 Years and Older | If a corticosteroid, such as dexamethasone, is co-administered, administer 50% of the recommended corticosteroid dose on Days 1 through 4 [see Clinical Studies (14.3)].†
5-HT3 antagonist | Adults and Pediatric Patients 12 Years and Older | See the selected 5-HT3 antagonist prescribing information for recommended dosage | none | none

* Administer aprepitant capsules 1 hour prior to chemotherapy treatment on Days 1, 2, and 3. If no chemotherapy is given on Days 2 and 3, administer aprepitant capsules in the morning.

† Administer dexamethasone 30 minutes prior to chemotherapy treatment on Day 1. A 50% dosage reduction of dexamethasone is recommended to account for a drug interaction with aprepitant [see Clinical Pharmacology (12.3)].

2.2 Prevention of Postoperative Nausea and Vomiting (PONV)

The recommended oral dosage of aprepitant capsules in adults is 40 mg within 3 hours prior to induction of anesthesia.

2.4 Administration Instructions

Aprepitant capsules can be administered with or without food.

Aprepitant capsules

- Swallow capsules whole.

3 DOSAGE FORMS AND STRENGTHS

Aprepitant Capsules, USP:

- 40 mg: hard gelatin capsules with a mustard yellow colored cap imprinted with a Glenmark logo 'G' in black ink and a white opaque colored body imprinted with '583' in black ink.
- 80 mg: hard gelatin capsules with a white opaque colored cap imprinted with a Glenmark logo 'G' in black ink and a white opaque colored body imprinted with '584' in black ink.
- 125 mg: hard gelatin capsules with a pink opaque colored cap imprinted with a Glenmark logo 'G' in black ink and a white opaque colored body imprinted with '585' in black ink.

4 CONTRAINDICATIONS

Aprepitant is contraindicated in patients:

- who are hypersensitive to any component of the product. Hypersensitivity reactions including anaphylactic reactions have been reported [see Adverse Reactions (6.2)].
- taking pimozide. Inhibition of CYP3A4 by aprepitant could result in elevated plasma concentrations of this drug which is a CYP3A4 substrate, potentially causing serious or life-threatening reactions, such as QT prolongation, a known adverse reaction of pimozide [see Warnings and Precautions (5.1)].

5 WARNINGS AND PRECAUTIONS

5.1 Clinically Significant CYP3A4 Drug Interactions

Aprepitant is a substrate, a weak-to-moderate (dose-dependent) inhibitor, and an inducer of CYP3A4.

- Use of aprepitant with other drugs that are CYP3A4 substrates, may result in increased plasma concentration of the concomitant drug.
  - Use of pimozide with aprepitant is contraindicated due to the risk of significantly increased plasma concentrations of pimozide, potentially resulting in prolongation of the QT interval, a known adverse reaction of pimozide [see Contraindications (4)].
- Use of aprepitant with strong or moderate CYP3A4 inhibitors (e.g., ketoconazole, diltiazem) may increase plasma concentrations of aprepitant and result in an increased risk of adverse reactions related to aprepitant.
- Use of aprepitant with strong CYP3A4 inducers (e.g., rifampin) may result in a reduction in aprepitant plasma concentrations and decreased efficacy of aprepitant.

See Table 10 and Table 11 for a listing of potentially significant drug interactions [see Drug Interactions (7.1, 7.2)].

5.2 Decrease in INR with Concomitant Warfarin

Coadministration of aprepitant with warfarin, a CYP2C9 substrate, may result in a clinically significant decrease in International Normalized Ratio (INR) of prothrombin time [see Clinical Pharmacology (12.3)]. Monitor the INR in patients on chronic warfarin therapy in the 2-week period, particularly at 7 to 10 days, following initiation of the 3-day regimen of aprepitant with each chemotherapy cycle, or following administration of a single 40 mg dose of aprepitant for the prevention of postoperative nausea and vomiting [see Drug Interactions (7.1)].

5.3 Risk of Reduced Efficacy of Hormonal Contraceptives

Upon coadministration with aprepitant, the efficacy of hormonal contraceptives may be reduced during administration of and for 28 days following the last dose of aprepitant [see Clinical Pharmacology (12.3)]. Advise patients to use effective alternative or back-up methods of contraception during treatment with aprepitant and for 1 month following the last dose of aprepitant [see Drug Interactions (7.1), Use in Specific Populations (8.3)].

6 ADVERSE REACTIONS

6.1 Clinical Trials Experience

Because clinical trials are conducted under widely varying conditions, adverse reaction rates observed in the clinical trials of a drug cannot be directly compared to rates in the clinical trials of another drug and may not reflect the rates observed in clinical practice.

The overall safety of aprepitant was evaluated in approximately 6800 individuals.

Adverse Reactions in Adults in the Prevention of Nausea and Vomiting Associated with HEC and MEC

In 2 active-controlled, double-blind clinical trials in patients receiving highly emetogenic chemotherapy (HEC) (Studies 1 and 2), aprepitant in combination with ondansetron and dexamethasone (aprepitant regimen) was compared to ondansetron and dexamethasone alone (standard therapy) [see Clinical Studies (14.1)].

In 2 active-controlled clinical trials in patients receiving moderately emetogenic chemotherapy (MEC) (Studies 3 and 4), aprepitant in combination with ondansetron and dexamethasone (aprepitant regimen) was compared to ondansetron and dexamethasone alone (standard therapy) [see Clinical Studies (14.2)]. The most common adverse reaction reported in patients who received MEC in pooled Studies 3 and 4 was dyspepsia (6% versus 4%).

Across these 4 studies there were 1412 patients treated with the aprepitant regimen during Cycle 1 of chemotherapy and 1099 of these patients continued into the Multiple-Cycle extension for up to 6 cycles of chemotherapy. The most common adverse reactions reported in patients who received HEC and MEC in pooled Studies 1, 2, 3 and 4 are listed in Table 5.

Table 3: Most Common Adverse Reactions in Patients Receiving HEC and MEC from a Pooled Analysis of HEC and MEC Studies*
 | Aprepitant, ondansetron, and dexamethasone† (N=1412) | Ondansetron and dexamethasone‡ (N=1396)
fatigue | 13% | 12%
diarrhea | 9% | 8%
asthenia | 7% | 6%
dyspepsia | 7% | 5%
abdominal pain | 6% | 5%
hiccups | 5% | 3%
white blood cell count decreased | 4% | 3%
dehydration | 3% | 2%
alanine aminotransferase increased | 3% | 2%

*Reported in ≥ 3% of patients treated with the aprepitant regimen and at a greater incidence than standard therapy.

†Aprepitant regimen

‡Standard therapy

In a pooled analysis of the HEC and MEC studies, less common adverse reactions reported in patients treated with the aprepitant regimen are listed in Table 6.

Table 4: Less Common Adverse Reactions in Aprepitant-Treated Patients from a Pooled Analysis of HEC and MEC Studies*
Infection and Infestations | oral candidiasis, pharyngitis
Blood and the Lymphatic System Disorders | anemia, febrile neutropenia, neutropenia, thrombocytopenia
Metabolism and Nutrition Disorders | decreased appetite, hypokalemia
Psychiatric Disorders | anxiety
Nervous System Disorders | dizziness, dysgeusia, peripheral neuropathy
Cardiac Disorders | palpitations
Vascular Disorders | flushing, hot flush
Respiratory, Thoracic and Mediastinal Disorders | cough, dyspnea, oropharyngeal pain
Gastrointestinal Disorders | dry mouth, eructation, flatulence, gastritis, gastroesophageal reflux disease, nausea, vomiting
Skin and Subcutaneous Tissue Disorders | alopecia, hyperhidrosis, rash
Musculoskeletal and Connective Tissue Disorders | musculoskeletal pain
General Disorders and Administration Site Condition | edema peripheral, malaise
Investigations | aspartate aminotransferase increased, blood alkaline phosphatase increased, blood sodium decreased, blood urea increased, proteinuria, weight decreased

*Reported in > 0.5% of patients treated with the aprepitant regimen, at a greater incidence than standard therapy and not previously described in Table 5.

In an additional active-controlled clinical study in 1169 patients receiving aprepitant and HEC, the adverse reactions were generally similar to that seen in the other HEC studies with aprepitant.

In another CINV study, Stevens-Johnson syndrome was reported as a serious adverse reaction in a patient receiving the aprepitant regimen with cancer chemotherapy.

Adverse reactions in the Multiple-Cycle extensions of HEC and MEC studies for up to 6 cycles of chemotherapy were generally similar to that observed in Cycle 1.

Adverse Reactions in Pediatric Patients 6 Months to 17 Years of Age in the Prevention of Nausea and Vomiting Associated with HEC or MEC

In a pooled analysis of 2 active-controlled clinical trials in pediatric patients aged 6 months to 17 years who received highly or moderately emetogenic cancer chemotherapy (Study 5 and a safety study, Study 6), aprepitant in combination with ondansetron with or without dexamethasone (aprepitant regimen) was compared to ondansetron with or without dexamethasone (control regimen).

There were 184 patients treated with the aprepitant regimen during Cycle 1 and 215 patients received open-label aprepitant for up to 9 additional cycles of chemotherapy.

In Cycle 1, the most common adverse reactions reported in pediatric patients treated with the aprepitant regimen in pooled Studies 5 and 6 are listed in Table 7.

Table 7: Most Common Adverse Reactions in Aprepitant -Treated Pediatric Patients in HEC and MEC Pooled Studies 5 and 6*

 | Aprepitant and ondansetron†; (N=184) | Ondansetron‡; (N=168)
neutropenia | 13% | 11%
headache | 9% | 5%
diarrhea | 6% | 5%
decreased appetite | 5% | 4%
cough | 5% | 3%
fatigue | 5% | 2%
hemoglobin decreased | 5% | 4%
dizziness | 5% | 1%
hiccups | 4% | 1%

*Reported in ≥3% of patients treated with the aprepitant regimen and at a greater incidence than control regimen.

† Aprepitant regimen

‡Control regimen

Forty-nine patients were treated with ifosfamide chemotherapy in each arm. Two of the patients treated with ifosfamide in the aprepitant arm developed behavioral changes (agitation = 1; abnormal behavior = 1), whereas no patient treated with ifosfamide in the control arm developed behavioral changes. Aprepitant has the potential for increasing ifosfamide-mediated neurotoxicity through induction of CYP3A4 [see Drug Interactions (7.1) and Clinical Pharmacology (12.3)].

Adverse Reactions in Adult Patients in the Prevention of PONV

In 2 active-controlled, double-blind clinical studies in patients receiving general anesthesia (Studies 7 and 8), 40 mg oral aprepitant was compared to 4 mg intravenous ondansetron [see Clinical Studies (14.4)].

There were 564 patients treated with aprepitant and 538 patients treated with ondansetron.

The most common adverse reactions reported in patients treated with aprepitant for PONV in pooled Studies 7 and 8 are listed in Table 8.

Table 5: Most Common Adverse Reactions in Aprepitant-Treated Patients in a Pooled Analysis of PONV Studies*
 | Aprepitant 40 mg (N = 564) | Ondansetron (N = 538)
constipation | 9% | 8%
hypotension | 6% | 5%

*Reported in ≥ 3% of patients treated with the aprepitant 40 mg and at a greater incidence than ondansetron.

In a pooled analysis of PONV studies, less common adverse reactions reported in patients treated with aprepitant are listed in Table 9.

Table 6: Less Common Adverse Reactions in Aprepitant-Treated Patients in a Pooled Analysis of PONV Studies*
Infections and Infestations | postoperative infection
Metabolism and Nutrition Disorders | hypokalemia, hypovolemia
Nervous System Disorders | dizziness, hypoesthesia, syncope
Cardiac Disorders | bradycardia
Vascular Disorders | hematoma
Respiratory, Thoracic and Mediastinal Disorders | dyspnea, hypoxia, respiratory depression
Gastrointestinal Disorders | abdominal pain, dry mouth, dyspepsia
Skin and Subcutaneous Tissue Disorders | urticaria
General Disorders and Administration Site Conditions | hypothermia
Investigations | blood albumin decreased, bilirubin increased, blood glucose increased, blood potassium decreased
Injury, Poisoning and Procedural Complications | operative hemorrhage, wound dehiscence

*Reported in > 0.5% of patients treated with aprepitant and at a greater incidence than ondansetron

In addition, two serious adverse reactions were reported in PONV clinical studies in patients taking a higher than recommended dose of aprepitant: one case of constipation, and one case of sub-ileus.

Other Studies

Angioedema and urticaria were reported as serious adverse reactions in a patient receiving aprepitant in a non-CINV/non-PONV study (aprepitant is only approved in the CINV and PONV populations).

6.2 Postmarketing Experience

The following adverse reactions have been identified during post-approval use of aprepitant. Because these reactions are reported voluntarily from a population of uncertain size, it is not always possible to reliably estimate their frequency or establish a causal relationship to drug exposure.

Skin and subcutaneous tissue disorders: pruritus, rash, urticaria, Stevens-Johnson syndrome/toxic epidermal necrolysis.

Immune system disorders: hypersensitivity reactions including anaphylactic reactions [see Contraindications (4)].

Nervous system disorders: ifosfamide-induced neurotoxicity reported after aprepitant and ifosfamide coadministration.

7 DRUG INTERACTIONS

7.1 Effect of Aprepitant on the Pharmacokinetics of Other Drugs

Aprepitant is a substrate, a weak-to-moderate (dose-dependent) inhibitor, and an inducer of CYP3A4. Aprepitant is also an inducer of CYP2C9 [see Clinical Pharmacology (12.3)].

Aprepitant acts as a moderate inhibitor of CYP3A4 when administered as a 3-day regimen (125 mg/80 mg/80 mg) and can increase plasma concentrations of concomitant drugs that are substrates for CYP3A4. Aprepitant acts as a weak inhibitor when administered as a single 40 mg dose and has not been shown to alter the plasma concentrations of concomitant drugs that are primarily metabolized through CYP3A4. Some substrates of CYP3A4 are contraindicated with aprepitant [see Contraindications (4)]. Dosage adjustment of some CYP3A4 and CYP2C9 substrates may be warranted, as shown in Table 10.

Table 7: Effects of Aprepitant on the Pharmacokinetics of Other Drugs
CYP3A4 Substrates
Pimozide
Clinical Impact | Increased pimozide exposure.
Intervention | Aprepitant is contraindicated [see Contraindications (4)].
Benzodiazepines
Clinical Impact | Increased exposure to midazolam or other benzodiazepines metabolized via CYP3A4 (alprazolam, triazolam) may increase the risk of adverse reactions [see Clinical Pharmacology (12.3)].
Intervention | 3-day aprepitant regimen; - Monitor for benzodiazepine-related adverse reactions. - Depending on the clinical situation (e.g., elderly patients) and degree of monitoring available, reduce the dose of intravenous midazolam; Single 40 mg dose of aprepitant; - No dosage adjustment of the benzodiazepine needed
Dexamethasone
Clinical Impact | Increased dexamethasone exposure [see Clinical Pharmacology (12.3)].
Intervention | 3-day aprepitant regimen; - Reduce the dose of oral dexamethasone by approximately 50% [see Dosage and Administration (2.1)].; Single 40 mg dose of aprepitant; - No dosage adjustment of oral dexamethasone needed
Methylprednisolone
Clinical Impact | Increased methylprednisolone exposure [see Clinical Pharmacology (12.3)].
Intervention | 3-day aprepitant regimen; - Reduce the dose of intravenous methylprednisolone by approximately 25% - Reduce the dose of oral methylprednisolone by approximately 50%; Single 40 mg dose of aprepitant; - No dosage adjustment of methylprednisolone needed
Chemotherapeutic agents that are metabolized by CYP3A4
Clinical Impact | Increased exposure of the chemotherapeutic agent may increase the risk of adverse reactions [see Clinical Pharmacology (12.3)].
Intervention | Vinblastine, vincristine, or ifosfamide or other chemotherapeutic agents; - Monitor for chemotherapeutic-related adverse reactions.; Etoposide, vinorelbine, paclitaxel, and docetaxel; - No dosage adjustment needed.
Hormonal Contraceptives
Clinical Impact | Decreased hormonal exposure during administration of and for 28 days after administration of the last dose of aprepitant [see Warnings and Precautions (5.3), Use in Specific Populations (8.3), Clinical Pharmacology (12.3)].
Intervention | Effective alternative or back-up methods of contraception (such as condoms and spermicides) should be used during treatment with aprepitant and for 1 month following the last dose of aprepitant.
Examples | birth control pills, skin patches, implants, and certain IUDs
CYP2C9 Substrates
Warfarin
Clinical Impact | Decreased warfarin exposure and decreased prothrombin time (INR) [see Warnings; and Precautions (5.2), Clinical Pharmacology (12.3)].
Intervention | In patients on chronic warfarin therapy, monitor the prothrombin time (INR) in the 2-week period, particularly at 7 to 10 days, following initiation of the 3-day aprepitant regimen with each chemotherapy cycle, or following administration of a single 40 mg dose of aprepitant.
Other
5-HT3 Antagonists
Clinical Impact | No change in the exposure of the 5-HT3 antagonist [see Clinical Pharmacology (12.3)].
Intervention | No dosage adjustment needed
Examples | ondansetron, granisetron, dolasetron

7.2 Effect of Other Drugs on the Pharmacokinetics of Aprepitant

Aprepitant is a CYP3A4 substrate [see Clinical Pharmacology (12.3)]. Co-administration of aprepitant with drugs that are inhibitors or inducers of CYP3A4 may result in increased or decreased plasma concentrations of aprepitant, respectively, as shown in Table 11.

Table 8: Effects of Other Drugs on Pharmacokinetics of Aprepitant
Moderate to Strong CYP3A4 Inhibitors
Clinical Impact | Significantly increased exposure of aprepitant may increase the risk of adverse reactions associated with aprepitant [see Adverse Reactions (6.1) and Clinical Pharmacology (12.3)].
Intervention | Avoid concomitant use of aprepitant
Examples | Moderate inhibitor: diltiazem; Strong inhibitors: ketoconazole, itraconazole, nefazodone, troleandomycin, clarithromycin, ritonavir, nelfinavir
Strong CYP3A4 Inducers
Clinical Impact | Substantially decreased exposure of aprepitant in patients chronically taking a strong CYP3A4 inducer may decrease the efficacy of aprepitant [see Clinical Pharmacology (12.3)].
Intervention | Avoid concomitant use of aprepitant
Examples | rifampin, carbamazepine, phenytoin

8 USE IN SPECIFIC POPULATIONS

8.1 Pregnancy

Risk Summary

There are insufficient data on use of aprepitant in pregnant women to inform a drug associated risk. In animal reproduction studies, no adverse developmental effects were observed in rats or rabbits exposed during the period of organogenesis to systemic drug levels (AUC) approximately 1.5 times the adult human exposure at the 125 mg/80 mg/80 mg aprepitant regimen [see Data].

The estimated background risk of major birth defects and miscarriage for the indicated populations is unknown. In the U.S. general population, the estimated background risk of major birth defects and miscarriage in clinically recognized pregnancies is 2 to 4% and 15 to 20%, respectively.

Data

Animal Data

In embryofetal development studies in rats and rabbits, aprepitant was administered during the period of organogenesis at oral doses up to 1000 mg/kg twice daily in rats and up to the maximum tolerated dose of 25 mg/kg/day in rabbits. No embryofetal lethality or malformations were observed at any dose level in either species. The exposures (AUC) in pregnant rats at 1000 mg/kg twice daily and in pregnant rabbits at 125 mg/kg/day were approximately 1.5 times the adult exposure at the 125 mg/80 mg/80 mg aprepitant regimen. Aprepitant crosses the placenta in rats and rabbits.

8.2 Lactation

Risk Summary

Lactation studies have not been conducted to assess the presence of aprepitant in human milk, the effects on the breastfed infant, or the effects on milk production. Aprepitant is present in rat milk. The developmental and health benefits of breastfeeding should be considered along with the mother's clinical need for aprepitant and any potential adverse effects on the breastfed infant from aprepitant or from the underlying maternal condition.

8.3 Females and Males of Reproductive Potential

Contraception

Upon administration of aprepitant, the efficacy of hormonal contraceptives may be reduced. Advise females of reproductive potential using hormonal contraceptives to use an effective alternative or back-up non-hormonal contraceptive (such as condoms and spermicides) during treatment with aprepitant and for 1 month following the last dose [see Drug Interactions (7.1), Clinical Pharmacology (12.3)].

8.4 Pediatric Use

Prevention of Nausea and Vomiting Associated with HEC or MEC

The safety and effectiveness of aprepitant capsules in pediatric patients 12 years of age and older for the prevention of acute and delayed nausea and vomiting associated with initial and repeat courses of HEC, including high-dose cisplatin, and MEC. Use of aprepitant in these age groups is supported by evidence from 302 pediatric patients in a randomized, double-blind, active comparator controlled clinical study (n = 207 patients aged6 month to less than 12 years n==95). Aprepitant was studied in combination with ondansetron with or without dexamethasone (at the discretion of the physician) [see Clinical Studies (14.3)]. Adverse reactions were similar to those reported in adult patients [see Adverse Reactions (6.1)].

The safety and effectiveness of aprepitant for the prevention of nausea and vomiting associated with HEC or MEC have not been established in patients less than 6 months.

Prevention of Postoperative Nausea and Vomiting (PONV)

The safety and effectiveness of aprepitant have not been established for the prevention of postoperative nausea and vomiting in pediatric patients.

Juvenile Animal Study

A study was conducted in young rats to evaluate the effects of aprepitant on growth and on neurobehavioral and sexual development. Rats were treated at oral doses up to the maximum feasible dose of 1000 mg/kg twice daily (providing exposure in male rats lower than the exposure at the recommended pediatric human dose and exposure in female rats equivalent to the pediatric human exposure) from the early postnatal period (Postnatal Day 10) through Postnatal Day 58. Slight changes in the onset of sexual maturation were observed in female and male rats; however, there were no effects on mating, fertility, embryonic-fetal survival, or histomorphology of the reproductive organs. There were no effects in neurobehavioral tests of sensory function, motor function, and learning and memory.

8.5 Geriatric Use

Of the 544 adult cancer patients treated with aprepitant in CINV clinical studies, 31% were aged 65 and over, while 5% were aged 75 and over. Of the 1120 adult cancer patients treated with aprepitant in PONV clinical studies, 7% were aged 65 and over, while 2% were aged 75 and over. Other reported clinical experience with aprepitant has not identified differences in responses between elderly and younger patients. In general, use caution when dosing elderly patients as they have a greater frequency of decreased hepatic, renal or cardiac function and concomitant disease or other drug therapy [see Clinical Pharmacology (12.3)].

8.6 Patients with Renal Impairment

The pharmacokinetics of aprepitant in patients with severe renal impairment and those with end stage renal disease (ESRD) requiring hemodialysis were similar to those of healthy subjects with normal renal function. No dosage adjustment is necessary for patients with any degree of renal impairment or for patients with ESRD undergoing hemodialysis.

8.7 Patients with Hepatic Impairment

The pharmacokinetics of aprepitant in patients with mild and moderate hepatic impairment were similar to those of healthy subjects with normal hepatic function. No dosage adjustment is necessary for patients with mild to moderate hepatic impairment (Child-Pugh score 5 to 9). There are no clinical or pharmacokinetic data in patients with severe hepatic impairment (Child-Pugh score greater than 9). Therefore, additional monitoring for adverse reactions in these patients may be warranted when aprepitant is administered [see Clinical Pharmacology (12.3)].

10 OVERDOSAGE

No specific information is available on the treatment of overdosage.

Drowsiness and headache were reported in one patient who ingested 1440 mg of aprepitant (approximately 11 times the maximum recommended single dose).

In the event of overdose, aprepitant should be discontinued and general supportive treatment and monitoring should be provided. Because of the antiemetic activity of aprepitant, drug-induced emesis may not be effective in cases of aprepitant overdosage.

Aprepitant is not removed by hemodialysis.

11 DESCRIPTION

Aprepitant Capsules USP contain the active ingredient aprepitant, USP. Aprepitant, USP is a substance P/neurokinin 1 (NK1) receptor antagonist, an antiemetic agent, chemically described as 5-[[(2R,3S)-2-[(1R)-1-[3,5-bis(trifluoromethyl)phenyl]ethoxy]-3-(4-fluorophenyl)-4-morpholinyl]methyl]-1,2-dihydro-3H-1,2,4-triazol-3-one.

Its empirical formula is C23H21F7N4O3, and its structural formula is:

Aprepitant, USP is a white to off-white powder, with a molecular weight of 534.43 g/mol. It is soluble in methanol and in acetone, sparingly soluble in ethanol, and practically insoluble in water.

Each capsule for oral administration contains either 40 mg, 80 mg, or 125 mg of aprepitant, USP and the following inactive ingredients: colloidal silicon dioxide, hydroxyethyl cellulose, microcrystalline cellulose, mannitol, poloxamer, povidone, sodium stearyl fumarate, vitamin E polyethylene glycol succinate, and purified water. The capsule shell excipients are gelatin, sodium lauryl sulphate and titanium dioxide. The 40-mg capsule shell also contains iron oxide yellow, and the 125 mg capsule also contains FD&C Red #3. Non-volatile solvents in the imprinting ink are shellac, iron oxide black and potassium hydroxide.

USP dissolution test pending.

12 CLINICAL PHARMACOLOGY

12.1 Mechanism of Action

Aprepitant is a selective high-affinity antagonist of human substance P/neurokinin 1 (NK1) receptors. Aprepitant has little or no affinity for serotonin (5-HT3), dopamine, and corticosteroid receptors, the targets of existing therapies for chemotherapy-induced nausea and vomiting (CINV) and postoperative nausea and vomiting (PONV).

Aprepitant has been shown in animal models to inhibit emesis induced by cytotoxic chemotherapeutic agents, such as cisplatin, via central actions. Animal and human Positron Emission Tomography (PET) studies with aprepitant have shown that it crosses the blood brain barrier and occupies brain NK1 receptors. Animal and human studies show that aprepitant augments the antiemetic activity of the 5-HT3-receptor antagonist ondansetron and the corticosteroid dexamethasone and inhibits both the acute and delayed phases of cisplatin-induced emesis.

12.2 Pharmacodynamics

NK1 Receptor Occupancy

In two single-blind, multiple-dose, randomized, and placebo-controlled studies, healthy young men received oral aprepitant doses of 10 mg (N=2), 30 mg (N=3), 100 mg (N=3) or 300 mg (N=5) once daily (0.08, 0.24, 0.8, and 2.4 times the maximum recommended single dose, respectively) for 14 days with 2 or 3 subjects on placebo. Both plasma aprepitant concentration and NK1 receptor occupancy in the corpus striatum by positron emission tomography were evaluated, at predose and 24 hours after the last dose. At aprepitant plasma concentrations of approximately 10 ng/mL and 100 ng/mL, the NK1 receptor occupancies were approximately 50% and 90%, respectively. The oral aprepitant regimen produced mean trough plasma aprepitant concentrations greater than 500 ng/mL in adults, which would be expected to, based on the fitted curve with the Hill equation, result in greater than 95% brain NK1 receptor occupancy. However, the receptor occupancy has not been determined. In addition, the relationship between NK1 receptor occupancy and the clinical efficacy of aprepitant has not been established.

Cardiac Electrophysiology

In a randomized, double-blind, positive-controlled, thorough QTc study, a single 200-mg dose of fosaprepitant had no effect on the QTc interval. Maximum aprepitant concentrations after a single 200-mg dose of fosaprepitant were 4- and 9-fold higher than that achieved with oral aprepitant 125 mg and 40 mg, respectively. QT prolongation with the oral aprepitant dosing regimens is not expected.

12.3 Pharmacokinetics

Absorption

Following oral administration of a single 40 mg dose of aprepitant in the fasted state, mean area under the plasma concentration-time curve (AUC0-∞) was 7.8 mcg•hr/mL and mean peak plasma concentration (Cmax) was 0.7 mcg/mL, occurring at approximately 3 hours postdose (Tmax). The absolute bioavailability at the 40 mg dose has not been determined.

Following oral administration of a single 125 mg dose of aprepitant on Day 1 and 80 mg once daily on Days 2 and 3, the AUC0-24hr was approximately 19.6 mcg•hr/mL and 21.2 mcg•hr/mL on Day 1 and Day 3, respectively. The Cmax of 1.6 mcg/mL and 1.4 mcg/mL were reached in approximately 4 hours (Tmax) on Day 1 and Day 3, respectively. At the dose range of 80 to 125 mg, the mean absolute oral bioavailability of aprepitant is approximately 60 to 65%. Oral administration of the capsule with a standard high-fat breakfast had no clinically meaningful effect on the bioavailability of aprepitant.

The pharmacokinetics of aprepitant were non-linear across the clinical dose range. In healthy young adults, the increase in AUC0-∞ was 26% greater than dose proportional between 80 mg and 125 mg single doses administered in the fed state.

Distribution

Aprepitant is greater than 95% bound to plasma proteins. The mean apparent volume of distribution at steady state (Vdss) was approximately 70 L in humans.

Aprepitant crosses the blood brain barrier in humans [see Clinical Pharmacology (12.1)].

Elimination

Metabolism

Aprepitant undergoes extensive metabolism. In vitro studies using human liver microsomes indicate that aprepitant is metabolized primarily by CYP3A4 with minor metabolism by CYP1A2 and CYP2C19. Metabolism is largely via oxidation at the morpholine ring and its side chains. No metabolism by CYP2D6, CYP2C9, or CYP2E1 was detected. In healthy young adults, aprepitant accounts for approximately 24% of the radioactivity in plasma over 72 hours following a single oral 300 mg dose of [^14C]-aprepitant (2.4 times the maximum recommended dose), indicating a substantial presence of metabolites in the plasma. Seven metabolites of aprepitant, which are only weakly active, have been identified in human plasma.

Excretion

Following administration of a single intravenous 100 mg dose of [^14C]-aprepitant prodrug to healthy subjects, 57% of the radioactivity was recovered in urine and 45% in feces. A study was not conducted with radiolabeled capsule formulation. The results after oral administration may differ.

Aprepitant is eliminated primarily by metabolism; aprepitant is not renally excreted. The apparent plasma clearance of aprepitant ranged from approximately 62 to 90 mL/min. The apparent terminal half-life ranged from approximately 9 to 13 hours.

Specific Populations

Geriatric Patients

Following oral administration of a single 125 mg dose of aprepitant on Day 1 and 80 mg once daily on Days 2 through 5 (2 additional days of dosing compared to the recommended duration), the AUC0-24hr of aprepitant was 21% higher on Day 1 and 36% higher on Day 5 in elderly (65 years and older) relative to younger adults. The Cmax was 10% higher on Day 1 and 24% higher on Day 5 in elderly relative to younger adults. These differences are not considered clinically meaningful [see Use in Specific Populations (8.5)].

Pediatric Patients

As part of a 3-day regimen, dosing of aprepitant capsules (125 mg/80 mg/80 mg) in 18 pediatric patients (aged 12 through 17 years) achieved a mean AUC0-24hr of 17 mcg•hr/mL on Day 1 with mean peak plasma concentration (Cmax) at 1.3 mcg/mL occurring at approximately 4 hours. The mean concentrations at the end of Day 2 (N=8) and Day 3 (N=16) were both at 0.6 mcg/mL.

A population pharmacokinetic analysis of aprepitant in pediatric patients (aged 6 months through 17 years) suggests that sex and race have no clinically meaningful effect on the pharmacokinetics of aprepitant.

Male and Female Patients

Following oral administration of a single dose of aprepitant ranging from 40 mg to 375 mg (3 times the maximum aprepitant recommended dose), the AUC0-24hr and Cmax are 9% and 17% higher in females as compared with males. The half-life of aprepitant is approximately 25% lower in females as compared with males and Tmax occurs at approximately the same time. These differences are not considered clinically meaningful.

Racial or Ethnic Groups

Following oral administration of a single dose of aprepitant ranging from 40 mg to 375 mg (3 times the maximum aprepitant recommended dose), the AUC0-24hr and Cmax are approximately 27% and 19% higher in Hispanics as compared with Caucasians. The AUC0-24hr and Cmax were 74% and 47% higher in Asians as compared to Caucasians. There was no difference in AUC0-24hr or Cmax between Caucasians and Blacks. These differences are not considered clinically meaningful.

Patients with Renal Impairment

A single 240 mg dose of aprepitant (approximately 1.9 times the maximum aprepitant recommended dose) was administered to patients with severe renal impairment (creatinine clearance less than 30 mL/min/1.73 m^2 as measured by 24-hour urinary creatinine clearance) and to patients with end stage renal disease (ESRD) requiring hemodialysis.

In patients with severe renal impairment, the AUC0-∞ of total aprepitant (unbound and protein bound) decreased by 21% and Cmax decreased by 32%, relative to healthy subjects (creatinine clearance greater than 80 mL/min estimated by Cockcroft-Gault method). In patients with ESRD undergoing hemodialysis, the AUC0-∞ of total aprepitant decreased by 42% and Cmax decreased by 32%. Due to modest decreases in protein binding of aprepitant in patients with renal disease, the AUC of pharmacologically active unbound drug was not significantly affected in patients with renal impairment compared with healthy subjects. Hemodialysis conducted 4 or 48 hours after dosing had no significant effect on the pharmacokinetics of aprepitant; less than 0.2% of the dose was recovered in the dialysate [see Use in Specific Populations (8.6)].

Patients with Hepatic Impairment

Following administration of a single 125 mg dose of aprepitant on Day 1 and 80 mg once daily on Days 2 and 3 to patients with mild hepatic impairment (Child-Pugh score 5 to 6), the AUC0-24hr of aprepitant was 11% lower on Day 1 and 36% lower on Day 3, as compared with healthy subjects given the same regimen. In patients with moderate hepatic impairment (Child-Pugh score 7 to 9), the AUC0-24hr of aprepitant was 10% higher on Day 1 and 18% higher on Day 3, as compared with healthy subjects given the same regimen. These differences in AUC0-24hr are not considered clinically meaningful. There are no clinical or pharmacokinetic data in patients with severe hepatic impairment (Child-Pugh score greater than 9) [see Use in Specific Populations (8.7)].

Body Mass Index (BMI)

For every 5 kg/m^2 increase in BMI, AUC0-24hr and Cmax of aprepitant decrease by 9% and 10%. BMI of subjects in the analysis ranged from 18 kg/m^2 to 36 kg/m^2. This change is not considered clinically meaningful.

Drug Interactions Studies

Aprepitant is a substrate, a moderate (dose-dependent) inhibitor, and an inducer of CYP3A4. Aprepitant is also an inducer of CYP2C9. Aprepitant is unlikely to interact with drugs that are substrates for the P-glycoprotein transporter.

Effects of Aprepitant on the Pharmacokinetics of Other Drugs

CYP3A4 substrates (i.e., midazolam): Interactions between aprepitant and coadministered midazolam are listed in Table 12 (increase is indicated as "↑", decrease as "↓", no change as "↔").

Table 9: Pharmacokinetic Interaction Data for Aprepitant and Coadministered Midazolam
Dosage of Aprepitant | Dosage of Midazolam | Observed Drug Interactions
Aprepitant 125 mg on Day 1 and 80 mg on Days 2 to 5 | oral 2 mg single dose on Days 1 and 5 | midazolam AUC ↑ 2.3-fold on Day 1 and ↑ 3.3-fold on Day 5 [see Drug Interactions (7.1)]
Aprepitant 125 mg on Day 1 and 80 mg on Days 2 and 3 | intravenous 2 mg prior to 3-day regimen of aprepitant and on Days 4, 8 and 15 | midazolam AUC ↑ 25% on Day 4, AUC ↓ 19% on Day 8 and AUC ↓ 4% on Day 15
Aprepitant 125 mg | intravenous 2 mg given 1 hour after aprepitant | midazolam AUC ↑ 1.5-fold
Aprepitant 40 mg | oral 2 mg | midazolam AUC ↑ 1.2-fold on Day 1

A difference of less than 2-fold increase of midazolam AUC is not considered clinically important.

Corticosteroids:

Dexamethasone: Aprepitant, when given as a regimen of 125 mg on Day 1 and 80 mg/day on Days 2 through 5, coadministered with 20 mg dexamethasone on Day 1 and 8 mg dexamethasone on Days 2 through 5, increased the AUC of dexamethasone by 2.2-fold on Days 1 and 5 [see Dosage and Administration (2.1)]. A single dose of aprepitant (40 mg) when coadministered with a single dose of dexamethasone 20 mg, increased the AUC of dexamethasone by 1.45-fold, which is not considered clinically significant.

Methylprednisolone: Aprepitant, when given as a regimen of 125 mg on Day 1 and 80 mg/day on Days 2 and 3, coadministered with 125 mg methylprednisolone IV on Day 1 and 40 mg methylprednisolone orally on Days 2 and 3, increased the AUC of methylprednisolone by 1.34-fold on Day 1 and by 2.5-fold on Day 3.

Chemotherapeutic agents:

Docetaxel: In a pharmacokinetic study, aprepitant (125 mg/80 mg/80 mg regimen) did not influence the pharmacokinetics of docetaxel.

Vinorelbine: In a pharmacokinetic study, aprepitant (125 mg/80 mg/80 mg regimen) did not influence the pharmacokinetics of vinorelbine to a clinically significant degree.

CYP2C9 substrates (Warfarin, Tolbutamide):

Warfarin: A single 125 mg dose of aprepitant was administered on Day 1 and 80 mg/day on Days 2 and 3 to healthy subjects who were stabilized on chronic warfarin therapy. Although there was no effect of aprepitant on the plasma AUC of R(+) or S(-) warfarin determined on Day 3, there was a 34% decrease in S(-) warfarin trough concentration accompanied by a 14% decrease in the prothrombin time (reported as International Normalized Ratio or INR) 5 days after completion of dosing with aprepitant [see Drug Interactions (7.1)].

Tolbutamide: Aprepitant, when given as 125 mg on Day 1 and 80 mg/day on Days 2 and 3, decreased the AUC of tolbutamide by 23% on Day 4, 28% on Day 8, and 15% on Day 15, when a single dose of tolbutamide 500 mg was administered prior to the administration of the 3-day regimen of aprepitant and on Days 4, 8, and 15. This effect was not considered clinically important.

Aprepitant, when given as a 40 mg single dose on Day 1, decreased the AUC of tolbutamide by 8% on Day 2, 16% on Day 4, 15% on Day 8, and 10% on Day 15, when a single dose of tolbutamide 500 mg was administered prior to the administration of aprepitant 40 mg and on Days 2, 4, 8, and 15. This effect was not considered significant.

Other Drugs

Oral contraceptives: When aprepitant was administered as a 3-day regimen (125 mg/80 mg/80 mg) with ondansetron and dexamethasone, and coadministered with an oral contraceptive containing ethinyl estradiol and norethindrone, the trough concentrations of both ethinyl estradiol and norethindrone were reduced by as much as 64% for 3 weeks post-treatment.

P-glycoprotein substrates: Aprepitant is unlikely to interact with drugs that are substrates for the P-glycoprotein transporter, as demonstrated by the lack of interaction of aprepitant with digoxin in a clinical drug interaction study.

5-HT3 antagonists: In clinical drug interaction studies, aprepitant did not have clinically important effects on the pharmacokinetics of ondansetron, granisetron, or hydrodolasetron (the active metabolite of dolasetron).

Effect of Other Drugs on the Pharmacokinetics of Aprepitant

Ketoconazole: When a single 125 mg dose of aprepitant was administered on Day 5 of a 10-day regimen of 400 mg/day of ketoconazole, a strong CYP3A4 inhibitor, the AUC of aprepitant increased approximately 5-fold and the mean terminal half-life of aprepitant increased approximately 3-fold [see Drug Interactions (7.2)].

Rifampin: When a single 375 mg dose of aprepitant (3 times the maximum aprepitant recommended dose) was administered on Day 9 of a 14-day regimen of 600 mg/day of rifampin, a strong CYP3A4 inducer, the AUC of aprepitant decreased approximately 11-fold and the mean terminal half-life decreased approximately 3-fold [see Drug Interactions (7.2)].

Diltiazem: In patients with mild to moderate hypertension, administration of aprepitant once daily, as a tablet formulation comparable to 230 mg of the capsule formulation (approximately 1.8 times the aprepitant recommended dose), with diltiazem 120 mg 3 times daily for 5 days, resulted in a 2-fold increase of aprepitant AUC and a simultaneous 1.7-fold increase of diltiazem AUC. These pharmacokinetic effects did not result in clinically meaningful changes in ECG, heart rate or blood pressure beyond those changes induced by diltiazem alone [see Drug Interactions (7.2)].

Paroxetine: Coadministration of once daily doses of aprepitant, as a tablet formulation comparable to 85 mg or 170 mg of the capsule formulation (approximately 0.7 and 1.4 times the aprepitant maximum recommended dose), with paroxetine 20 mg once daily, resulted in a decrease in AUC by approximately 25% and Cmax by approximately 20% of both aprepitant and paroxetine. This effect was not considered clinically important.

13 NONCLINICAL TOXICOLOGY

13.1 Carcinogenesis, Mutagenesis, Impairment of Fertility

Carcinogenesis

Carcinogenicity studies were conducted in Sprague-Dawley rats and in CD-1 mice for 2 years. In the rat carcinogenicity studies, animals were treated with oral doses ranging from 0.05 to 1000 mg/kg twice daily. The highest dose produced a systemic exposure to aprepitant (AUC) of 0.7 to 1.6 times the adult human exposure at the 125 mg/80 mg/80 mg aprepitant regimen. Treatment with aprepitant at doses of 5 to 1000 mg/kg twice daily caused an increase in the incidences of thyroid follicular cell adenomas and carcinomas in male rats. In female rats, it produced hepatocellular adenomas at 5 to 1000 mg/kg twice daily and hepatocellular carcinomas and thyroid follicular cell adenomas at 125 to 1000 mg/kg twice daily. In the mouse carcinogenicity studies, the animals were treated with oral doses ranging from 2.5 to 2000 mg/kg/day. The highest dose produced a systemic exposure of about 2.8 to 3.6 times the adult human exposure at the 125 mg/80 mg/80 mg aprepitant regimen. Treatment with aprepitant produced skin fibrosarcomas at 125 and 500 mg/kg/day doses in male mice.

Mutagenesis

Aprepitant was not genotoxic in the Ames test, the human lymphoblastoid cell (TK6) mutagenesis test, the rat hepatocyte DNA strand break test, the Chinese hamster ovary (CHO) cell chromosome aberration test and the mouse micronucleus test.

Impairment of Fertility

Aprepitant did not affect the fertility or general reproductive performance of male or female rats at doses up to the maximum feasible dose of 1000 mg/kg twice daily (providing exposure in male rats lower than the exposure at the recommended adult human dose and exposure in female rats at about 1.6 times the adult human exposure at the 125 mg/80 mg/80 mg aprepitant regimen).

14 CLINICAL STUDIES

14.1 Prevention of Nausea and Vomiting Associated with HEC in Adults

Oral administration of aprepitant in combination with ondansetron and dexamethasone (aprepitant regimen) has been shown to prevent acute and delayed nausea and vomiting associated with HEC including high-dose cisplatin, and nausea and vomiting associated with MEC.

In Studies 1 and 2, both multicenter, randomized, parallel, double-blind, controlled clinical studies in adults, aprepitant in combination with ondansetron and dexamethasone was compared with standard therapy (ondansetron and dexamethasone alone) in patients receiving a chemotherapy regimen that included cisplatin greater than 50 mg/m^2 (mean cisplatin dose = 80.2 mg/m^2). See Table 13.

In these studies, 95% of the patients in the aprepitant group received a concomitant chemotherapeutic agent in addition to protocol-mandated cisplatin. The most common chemotherapeutic agents and the number of aprepitant patients exposed follows: etoposide (106), fluorouracil (100), gemcitabine (89), vinorelbine (82), paclitaxel (52), cyclophosphamide (50), doxorubicin (38), docetaxel (11).

Of the 550 patients who were randomized to receive the aprepitant regimen, 42% were women, 58% men, 59% White, 3% Asian, 5% Black, 12% Hispanic American, and 21% Multi-Racial. The aprepitant-treated patients in these clinical studies ranged from 14 to 84 years of age, with a mean age of 56 years. A total of 170 patients were 65 years or older, with 29 patients being 75 years or older.

Table 10: HEC Treatment Regimens – Studies 1 and 2*
 | Day 1 | Day 2 | Day 3 | Day 4
CINV Aprepitant Regimen
Oral Aprepitant† | 125 mg | 80 mg | 80 mg | none
Oral Dexamethasone‡ | 12 mg | 8 mg | 8 mg | 8 mg
Ondansetron | 5-HT3 antagonist§ | none | none | none
CINV Standard Therapy
Oral Dexamethasone | 20 mg | 8 mg twice daily | 8 mg twice daily | 8 mg twice daily
Ondansetron | 5-HT3 antagonist§ | none | none | none

*Aprepitant placebo and dexamethasone placebo were used to maintain blinding.

†Aprepitant was administered 1 hour prior to chemotherapy treatment on Day 1 and in the morning on Days 2 and 3.

‡Dexamethasone was administered 30 minutes prior to chemotherapy treatment on Day 1 and in the morning on Days 2 through 4. The 12 mg dose of dexamethasone on Day 1 reflects a dosage adjustment to account for a drug interaction with the aprepitant regimen [see Clinical Pharmacology (12.3)].

§Ondansetron 32 mg intravenous was used in the clinical trials of aprepitant. Although this dose was used in clinical trials, this is no longer the currently recommended dose. Refer to the ondansetron prescribing information for the current recommended dose.

The antiemetic activity of aprepitant was evaluated during the acute phase (0 to 24 hours post-cisplatin treatment), the delayed phase (25 to 120 hours post-cisplatin treatment) and overall (0 to 120 hours post-cisplatin treatment) in Cycle 1. Efficacy was based on evaluation of the following endpoints in which emetic episodes included vomiting, retching, or dry heaves:

Primary endpoint:

- complete response (defined as no emetic episodes and no use of rescue therapy as recorded in patient diaries)
Other prespecified endpoints:
- complete protection (defined as no emetic episodes, no use of rescue therapy, and a maximum nausea visual analogue scale [VAS] score less than 25 mm on a 0 to 100 mm scale)
- no emesis (defined as no emetic episodes regardless of use of rescue therapy)
- no nausea (maximum VAS less than 5 mm on a 0 to 100 mm scale)
- no significant nausea (maximum VAS less than 25 mm on a 0 to 100 mm scale)

A summary of the key study results from each individual study analysis is shown in Table 14. In both studies, a statistically significantly higher proportion of patients receiving the aprepitant regimen in Cycle 1 had a complete response in the overall phase (primary endpoint), compared with patients receiving standard therapy. A statistically significant difference in complete response in favor of the aprepitant regimen was also observed when the acute phase and the delayed phase were analyzed separately.

Table 11: Percent of Patients Receiving HEC Responding by Treatment Group and Phase — Cycle 1
 | Study 1 |  |  | Study 2
ENDPOINTS | Aprepitant Regimen (N=260)* % | Standard Therapy (N=261)* % | p-Value | Aprepitant Regimen (N=261)* % | Standard Therapy (N=263)* % | p-Value
PRIMARY ENDPOINT
Complete Response
Overall† | 73 | 52 | <0.001 | 63 | 43 | <0.001
OTHER PRESPECIFIED ENDPOINTS
Complete Response
Acute phase‡ Delayed phase§ | 89 75 | 78 56 | <0.001 <0.001 | 83 68 | 68 47 | <0.001 <0.001
Complete Protection
Overall Acute phase Delayed phase | 63 85 66 | 49 75 52 | 0.001 NS¶ <0.001 | 56 80 61 | 41 65 44 | <0.001 <0.001 <0.001
No Emesis
Overall Acute phase Delayed phase | 78 90 81 | 55 79 59 | <0.001 0.001 <0.001 | 66 84 72 | 44 69 48 | <0.001 <0.001 <0.001
No Nausea
Overall Delayed phase | 48 51 | 44 48 | NS# NS# | 49 53 | 39 40 | NS¶ NS¶
No Significant Nausea
Overall Delayed phase | 73 75 | 66 69 | NS# NS# | 71 73 | 64 65 | NS# NS#

Visual analogue scale (VAS) score range: 0 mm=no nausea; 100 mm=nausea as bad as it could be.

*N: Number of patients (older than 18 years of age) who received cisplatin, study drug, and had at least one post-treatment efficacy evaluation.

†Overall: 0 to 120 hours post-cisplatin treatment.

‡Acute phase: 0 to 24 hours post-cisplatin treatment.

§Delayed phase: 25 to 120 hours post-cisplatin treatment.

¶Not statistically significant when adjusted for multiple comparisons.

#Not statistically significant.

In both studies, the estimated time to first emesis after initiation of cisplatin treatment was longer with the aprepitant regimen, and the incidence of first emesis was reduced in the aprepitant regimen group compared with standard therapy group as depicted in the Kaplan-Meier curves in Figure 1.

Figure 1: Percent of Patients Receiving HEC Who Remain Emesis Free Over Time — Cycle 1

p-Value <0.001 based on a log rank test for Study 1 and Study 2; nominal p-values not adjusted for multiplicity.

Additional Patient-Reported Outcomes: The impact of nausea and vomiting on patients' daily lives was assessed in Cycle 1 of both studies using the Functional Living Index–Emesis (FLIE), a validated nausea-and vomiting-specific patient-reported outcome measure. Minimal or no impact of nausea and vomiting on patients' daily lives is defined as a FLIE total score greater than 108. In each of the 2 studies, a higher proportion of patients receiving the aprepitant regimen reported minimal or no impact of nausea and vomiting on daily life (Study 1: 74% versus 64%; Study 2: 75% versus 64%).

Multiple-Cycle Extension: In the same 2 clinical studies, patients continued into the Multiple-Cycle extension for up to 5 additional cycles of chemotherapy. The proportion of patients with no emesis and no significant nausea by treatment group at each cycle is depicted in Figure 2. Antiemetic effectiveness for the patients receiving the aprepitant regimen was maintained throughout repeat cycles for those patients continuing in each of the multiple cycles.

Figure 2: Proportion of Patients Receiving HEC with No Emesis and No Significant Nausea by Treatment Group and Cycle

14.2 Prevention of Nausea and Vomiting Associated with MEC in Adults

Aprepitant was studied in two randomized, double-blind, parallel-group studies (Studies 3 and 4) in adult patients receiving MEC.

In Study 3, in breast cancer patients, aprepitant in combination with ondansetron and dexamethasone was compared with standard therapy (ondansetron and dexamethasone) in patients receiving a MEC regimen that included cyclophosphamide 750 to 1500 mg/m^2; or cyclophosphamide 500 to 1500 mg/m^2 and doxorubicin (less than or equal to 60 mg/m^2) or epirubicin (less than or equal to 100 mg/m^2). See Table 15.

In this study, the most common combinations were cyclophosphamide + doxorubicin (61%); and cyclophosphamide + epirubicin + fluorouracil (22%).

Of the 438 patients who were randomized to receive the aprepitant regimen, 99.5% were women. Of these, approximately 80% were White, 8% Black, 8% Asian, 4% Hispanic, and less than 1% Other. The aprepitant-treated patients in this clinical study ranged from 25 to 78 years of age, with a mean age of 53 years; 70 patients were 65 years or older, with 12 patients being over 74 years.

Table 12: MEC Treatment Regimens – Studies 3 and 4*
 | Day 1 | Day 2 | Day 3
CINV Aprepitant Regimen
Oral Aprepitant† | 125 mg | 80 mg | 80 mg
Oral Dexamethasone | 12 mg‡ | none | none
Oral Ondansetron | 8 mg × 2 doses§ | none | none
CINV Standard Therapy
Oral Dexamethasone | 20 mg‡ | none | none
Oral Ondansetron | 8 mg × 2 doses§ | 8 mg twice daily | 8 mg twice daily

*Aprepitant placebo and dexamethasone placebo were used to maintain blinding.

†Aprepitant was administered 1 hour prior to chemotherapy treatment on Day 1 and in the mornings on Days 2 and 3.

‡Dexamethasone was administered 30 minutes prior to chemotherapy treatment on Day 1. The 12 mg dose of dexamethasone on Day 1 reflects a dosage adjustment to account for a drug interaction with the aprepitant regimen [see Clinical Pharmacology (12.3)].

§The first ondansetron dose was administered 30 to 60 minutes prior to chemotherapy treatment on Day 1 and the second dose was administered 8 hours after first ondansetron dose.

The antiemetic activity of aprepitant was evaluated based on the following endpoints in which emetic episodes included vomiting, retching, or dry heaves:

Primary endpoint:
Other prespecified endpoints:

- complete response (defined as no emetic episodes and no use of rescue therapy as recorded in patient diaries) in the overall phase (0 to 120 hours post-chemotherapy)
Other prespecified endpoints:
- no emesis (defined as no emetic episodes regardless of use of rescue therapy)
- no nausea (maximum VAS less than 5 mm on a 0 to 100 mm scale)
- no significant nausea (maximum VAS less than 25 mm on a 0 to 100 mm scale)
- complete protection (defined as no emetic episodes, no use of rescue therapy, and a maximum nausea visual analogue scale [VAS] score less than 25 mm on a 0 to 100 mm scale)
- complete response during the acute and delayed phases.

A summary of the key results from Study 3 is shown in Table 16. In Study 3, a statistically significantly (p=0.015) higher proportion of patients receiving the aprepitant regimen (51%) in Cycle 1 had a complete response (primary endpoint) during the overall phase compared with patients receiving standard therapy (42%). The difference between treatment groups was primarily driven by the "No Emesis Endpoint", a principal component of this composite primary endpoint. In addition, a higher proportion of patients receiving the aprepitant regimen in Cycle 1 had a complete response during the acute (0 to 24 hours) and delayed (25 to 120 hours) phases compared with patients receiving standard therapy; however, the treatment group differences failed to reach statistical significance, after multiplicity adjustments.

Table 13: Percent of Patients Receiving MEC Responding by Treatment Group and Phase — Cycle 1 of Study 3
ENDPOINTS | Aprepitant Regimen (N=433)* % | Standard Therapy (N=424)* % | p-Value
PRIMARY ENDPOINT†
Complete Response | 51 | 42 | 0.015
OTHER PRESPECIFIED ENDPOINTS†
No Emesis | 76 | 59 | NS‡
No Nausea | 33 | 33 | NS
No Significant Nausea | 61 | 56 | NS
No Rescue Therapy | 59 | 56 | NS
Complete Protection | 43 | 37 | NS

*N: Number of patients included in the primary analysis of complete response.

†Overall: 0 to 120 hours post-chemotherapy treatment.

‡NS when adjusted for prespecified multiple comparisons rule; unadjusted p-value <0.001.

Additional Patient-Reported Outcomes: In Study 3, in patients receiving MEC, the impact of nausea and vomiting on patients' daily lives was assessed in Cycle 1 using the FLIE. A higher proportion of patients receiving the aprepitant regimen reported minimal or no impact on daily life (64% versus 56%). This difference between treatment groups was primarily driven by the "No Vomiting Domain" of this composite endpoint.

Multiple-Cycle Extension: In Study 3, patients receiving MEC were permitted to continue into the Multiple-Cycle extension of the study for up to 3 additional cycles of chemotherapy. The antiemetic effect for patients receiving the aprepitant regimen was maintained during all cycles.

In Study 4, aprepitant in combination with ondansetron and dexamethasone was compared with a standard therapy (ondansetron and dexamethasone alone) in patients receiving a MEC regimen that included any intravenous dose of oxaliplatin, carboplatin, epirubicin, idarubicin, ifosfamide, irinotecan, daunorubicin, doxorubicin; cyclophosphamide intravenous (less than 1500 mg/m^2); or cytarabine intravenous (greater than 1 g/m^2). See Table 15. Patients receiving the aprepitant regimen were receiving chemotherapy for a variety of tumor types including 50% with breast cancer, 21% with gastrointestinal cancers including colorectal cancer, 13% with lung cancer and 6% with gynecological cancers.

Of the 430 patients who were randomized to receive the aprepitant regimen, 76% were women and 24% were men. The distribution by race was 67% White, 6% Black or African American, 11% Asian, and 12% multiracial. Classified by ethnicity, 36% were Hispanic and 64% were non-Hispanic. The aprepitant-treated patients in this clinical study ranged from 22 to 85 years of age, with a mean age of 57 years; approximately 59% of the patients were 55 years or older with 32 patients being over 74 years.

The antiemetic activity of aprepitant was evaluated based on no vomiting (with or without rescue therapy) in the overall period (0 to 120 hours post-chemotherapy) and complete response (defined as no vomiting and no use of rescue therapy) in the overall period.

A summary of the key results from Study 4 is shown in Table 17. In Study 4, a statistically significantly higher proportion of patients receiving the aprepitant regimen (76%) in Cycle 1 had no vomiting during the overall phase compared with patients receiving standard therapy (62%). In addition, a higher proportion of patients receiving the aprepitant regimen (69%) in Cycle 1 had a complete response in the overall phase (0 to 120 hours) compared with patients receiving standard therapy (56%). In the acute phase (0 to 24 hours following initiation of chemotherapy), a higher proportion of patients receiving aprepitant compared to patients receiving standard therapy were observed to have no vomiting (92% and 84%, respectively) and complete response (89% and 80%, respectively). In the delayed phase (25 to 120 hours following initiation of chemotherapy), a higher proportion of patients receiving aprepitant compared to patients receiving standard therapy were observed to have no vomiting (78% and 67%, respectively) and complete response (71% and 61%, respectively).

In a subgroup analysis by tumor type, a numerically higher proportion of patients receiving aprepitant were observed to have no vomiting and complete response compared to patients receiving standard therapy. For sex, the difference in complete response rates between the aprepitant and standard regimen groups was 14% in females (64.5% and 50.3%, respectively) and 4% in males (82.2% and 78.2%, respectively) during the overall phase. A similar difference for sex was observed for the no vomiting endpoint.

Table 14: Percent of Patients Receiving MEC Responding by Treatment Group — Cycle 1 of Study 4
ENDPOINTS | Aprepitant Regimen (N=430)* % | Standard Therapy (N=418)* % | p-Value
No Vomiting Overall | 76 | 62 | <0.0001
Complete Response Overall | 69 | 56 | 0.0003

*N = Number of patients who received chemotherapy treatment, study drug, and had at least one post-treatment efficacy evaluation.

14.3 Prevention of Nausea and Vomiting Associated with HEC or MEC in Pediatric Patients

In a randomized, double-blind, active comparator-controlled clinical study that included 302 pediatric patients aged 6 months to 17 years receiving HEC or MEC, aprepitant in combination with ondansetron was compared to ondansetron alone (control regimen) for the prevention of CINV (Study 5). Intravenous dexamethasone was permitted as part of the antiemetic regimen in both treatment groups, at the discretion of the physician. A 50% dose reduction of dexamethasone was required for patients in the aprepitant group, reflecting a dosage adjustment to account for a drug interaction [see Clinical Pharmacology (12.3)]. No dexamethasone dose reduction was required for patients who received the control regimen.

Eligible patients had documented malignancy at either an original diagnosis or relapse and were scheduled to receive emetogenic chemotherapy or a chemotherapy regimen not previously tolerated due to vomiting along with ondansetron as part of their antiemetic regimen.

Of the 152 pediatric patients randomized to receive the aprepitant regimen, 55% were male, 45% female, 78% White, 7% Asian, 0% Black, 24% Hispanic, and 13% Multi-Racial. The most common primary malignancies in subjects receiving the aprepitant regimen were osteosarcoma (11%), Ewing’s sarcoma (11%), neuroblastoma (9%) and rhabdomyosarcoma (8%). Other concomitant chemotherapy agents commonly administered and the number of aprepitant patients exposed were: vincristine sulfate (65), etoposide (59), doxorubicin (48), ifosfamide (45), carboplatin (39), and cisplatin (35).

The treatment regimens in Study 5 for pediatric patients are defined in Table 18. Of the pediatric patients, 29% in the aprepitant regimen and 28% in the control regimen used dexamethasone as part of the antiemetic regimen in Cycle 1.

Table 18: HEC and MEC Treatment Regimens* for Pediatric Patients 6 Months to 17 Years of Age— Study 5

 | Day 1 | Day 2 | Day 3
CINV aprepitant Regimen
Pediatric Patients 6 Months to less than 12 Years of Age | 3 mg/kg body weight oral suspension | 2 mg/kg body weight oral suspension | 2 mg/kg body weight oral suspension
Pediatric Patients 12 to 17 Years of Age† | 125 mg capsule | 80 mg capsule | 80 mg capsule
Ondansetron | Per standard of care | none | none
CINV Control Regimen
Ondansetron | Per standard of care‡ | none | none

*Intravenous dexamethasone was permitted at the discretion of the physician. A 50% dose reduction of dexamethasone was required for patients in the aprepitant group, reflecting a dosage adjustment to account for a drug interaction [see Clinical Pharmacology (12.3)]. No dexamethasone dose reduction was required for patients in the control regimen.
†Aprepitant was administered 1 hour prior to chemotherapy treatment on Days 1, 2, and 3. If no chemotherapy was given on Days 2 and 3, aprepitant was administered in the morning.

‡Ondansetron was administered 30 minutes prior to chemotherapy on Day 1§aprepitant placebo was used to maintain blinding.

The antiemetic activity of aprepitant was evaluated over a 5-day (120 hour) period following the initiation of chemotherapy on Day 1. The primary endpoint in Study 5 was complete response in the delayed phase (25 to 120 hours following chemotherapy) in Cycle 1. Patients had the opportunity to receive open-label aprepitant in subsequent cycles (Optional Cycles 2-6); however, efficacy was not assessed in these optional cycles. Overall efficacy was based on the evaluation of the following endpoints:

Primary endpoint:

- complete response (no vomiting, retching and no use of rescue medication) in the delayed phase (25 to 120 hours following initiation of chemotherapy) Other prespecified endpoints:
- complete response in the acute phase (0 to 24 hours following initiation of chemotherapy)
- complete response in the overall phase (up to 120 hours following initiation of chemotherapy)
- no vomiting (defined as no emesis, retching or dry heaves, regardless of use of rescue medication) in the overall phase
- safety and tolerability

A summary of the key study results are shown in Table 19.

Table 19: Percent of Patients Who Responded to Treatment by Treatment Group and Phase – Cycle 1 of Study 5

 | Aprepitant; Regimen; n/m (%) | Control; Regimen; n/m (%)
PRIMARY ENDPOINT
Complete Response - Delayed phase | 77/152 (50.7) | 39/150 (26.0)
OTHER PRESPECIFIED ENDPOINTS
Complete Response* – Acute phase | 101/152 (66.4) | 78/150 (52.0)
Complete Response* – Overall phase | 61/152 (40.1)† | 30/150 (20.0)

*Complete Response = No vomiting or retching and no use of rescue medication.

†p<0.01 when compared to Control Regimen

‡ p<0.05 when compared to Control Regimen n/m = Number of patients with desired response/number of patients included in time point. Acute Phase: 0 to 24 hours following initiation of chemotherapy. Delayed Phase: 25 to 120 hours following initiation of chemotherapy. Overall Phase: 0 to 120 hours following initiation of chemotherapy.

14.4 Prevention of PONV in Adults

In two multicenter, randomized, double-blind, active comparator-controlled, parallel-group clinical studies (Studies 7 and 8), aprepitant was compared with ondansetron for the prevention of postoperative nausea and vomiting in 1658 patients undergoing open abdominal surgery. These two studies were of similar design; however, they differed in terms of study hypothesis, efficacy analyses and geographic location. Study 7 was a multinational study including the U.S., whereas, Study 8 was conducted entirely in the U.S.

In the two studies, patients were randomized to receive 40 mg aprepitant, 125 mg aprepitant, or 4 mg ondansetron as a single dose. Aprepitant was given orally with 50 mL of water 1 to 3 hours before anesthesia. Ondansetron was given intravenously immediately before induction of anesthesia. A comparison between the aprepitant 125 mg dose did not demonstrate any additional clinical benefit over the 40 mg dose and is not a recommended dosage regimen [see Dosage and Administration (2.2)].

Of the 564 patients who received 40 mg aprepitant, 92% were women and 8% were men; of these, 58% were White, 13% Hispanic American, 7% Multi-Racial, 14% Black, 6% Asian, and 2% Other. The age of patients treated with 40 mg aprepitant ranged from 19 to 84 years, with a mean age of 46.1 years. 46 patients were 65 years or older, with 13 patients being 75 years or older.

The antiemetic activity of aprepitant was evaluated during the 0 to 48 hour period following the end of surgery.

Efficacy measures in Study 7 included:

- no emesis (defined as no emetic episodes regardless of use of rescue therapy) in the 0 to 24 hours following the end of surgery (primary)
- complete response (defined as no emetic episodes and no use of rescue therapy) in the 0 to 24 hours following the end of surgery (primary)
- no emesis (defined as no emetic episodes regardless of use of rescue therapy) in the 0 to 48 hours following the end of surgery (secondary)
- time to first use of rescue medication in the 0 to 24 hours following the end of surgery (exploratory)
- time to first emesis in the 0 to 48 hours following the end of surgery (exploratory).

A closed testing procedure was applied to control the type I error for the primary endpoints.

The results of the primary and secondary endpoints for 40 mg aprepitant and 4 mg ondansetron are described in Table 20:

Table 20: Response Rates for Select Efficacy Endpoints (Modified-Intention-to-Treat Population) – Study 7

Treatment | n/m (%) | Aprepitant vs. Ondansetron
Treatment | n/m (%) | Δ | Odds ratio* | Analysis
PRIMARY ENDPOINTS
No Vomiting 0 to 24 hours (Superiority)
(no emetic episodes)
Aprepitant 40 mg | 246/293 (84.0) | 12.6% | 2.1 | P<0.001†
Ondansetron | 200/280 (71.4)
Complete Response (Non-inferiority: If LB‡ >0.65)
(no emesis and no rescue therapy, 0 to 24 hours)
Aprepitant 40 mg | 187/293 (63.8) | 8.8% | 1.4 | LB=1.02
Ondansetron | 154/280 (55.0)
Complete Response (Superiority: If LB >1.0)
(no emesis and no rescue therapy, 0 to 24 hours)
Aprepitant 40 mg | 187/293 (63.8) | 8.8% | 1.4 | LB=1.02‡
Ondansetron | 154/280 (55.0)
SECONDARY ENDPOINT
No Vomiting 0 to 48 hours (Superiority)
(no emetic episodes)
Aprepitant 40 mg | 238/292 (81.5) | 15.2% | 2.3 | P<0.001§
Ondansetron | 185/279 (66.3)
n/m = Number of responders/number of patients in analysis.
Δ Difference (%): Aprepitant 40 mg minus Ondansetron.

*Estimated odds ratio for aprepitant versus Ondansetron. A value of >1 favors aprepitant over Ondansetron.

†P-value of two-sided test <0.05.

‡LB = lower bound of 1-sided 97.5% confidence interval for the odds ratio.

§Based on the prespecified fixed sequence multiplicity strategy, aprepitant 40 mg was not superior to Ondansetron.

In Study 7, the use of aprepitant did not affect the time to first use of rescue medication when compared to ondansetron. However, compared to the ondansetron group, use of aprepitant delayed the time to first vomiting, as depicted in Figure 3.

Figure 3: Percent of Patients Who Remain Emesis Free During the 48 Hours Following End of Surgery – Study 7

Efficacy measures in Study 8 included:

- complete response (defined as no emetic episodes and no use of rescue therapy) in the 0 to 24 hours following the end of surgery (primary)
- no emesis (defined as no emetic episodes regardless of use of rescue therapy) in the 0 to 24 hours following the end of surgery (secondary)
- no use of rescue therapy in the 0 to 24 hours following the end of surgery (secondary)
- no emesis (defined as no emetic episodes regardless of use of rescue therapy) in the 0 to 48 hours following the end of surgery (secondary).

Study 8 failed to satisfy its primary hypothesis that aprepitant is superior to ondansetron in the prevention of PONV as measured by the proportion of patients with complete response in the 24 hours following end of surgery.

The study demonstrated that 40 mg aprepitant had a clinically meaningful effect with respect to the secondary endpoint "no vomiting" during the first 24 hours after surgery and was associated with a 16% improvement over ondansetron for the no vomiting endpoint.

Table 21: Response Rates for Select Efficacy Endpoints (Modified-Intention-to-Treat

Population) – Study 8

Treatment | n/m (%) | Aprepitant vs. Ondansetron
Treatment | n/m (%) | Δ | Odds ratio* | Analysis
PRIMARY ENDPOINT
Complete Response
(no emesis and no rescue therapy, 0 to 24 hours)
Aprepitant 40 mg | 111/248 (44.8) | 2.5% | 1.1 | 0.61
Ondansetron | 104/246 (42.3)
SECONDARY ENDPOINTS
No Vomiting
(no emetic episodes, 0 to 24 hours)
Aprepitant 40 mg | 223/248 (89.9) | 16.3% | 3.2 | <0.001†
Ondansetron | 181/246 (73.6)
No Use of Rescue Medication
(for established emesis or nausea, 0 to 24 hours)
Aprepitant 40 mg | 112/248 (45.2) | -0.7% | 1.0 | 0.83
Ondansetron | 113/246 (45.9)
No Vomiting 0 to 48 hours (Superiority)
(no emetic episodes, 0 to 48 hours)
Aprepitant 40 mg | 209/247 (84.6) | 17.7% | 2.7 | <0.001*
Ondansetron | 164/245 (66.9)

n/m = Number of responders/number of patients in analysis.

Δ Difference (%): Aprepitant 40 mg minus Ondansetron.

*Estimated odds ratio: Aprepitant 40 mg versus Ondansetron.

†Not statistically significant after pre-specified multiplicity adjustment.

16 HOW SUPPLIED/STORAGE AND HANDLING

Aprepitant Capsules USP, 125 mg: hard gelatin capsules with a pink opaque colored cap imprinted with a Glenmark logo 'G' in black ink and a white opaque colored body imprinted with '585' in black ink. They are supplied as follows:

NDC 68462-585-76 Carton of 6 capsules (containing 1 x 6 unit-dose blisters)

Aprepitant Capsules USP, 80 mg: hard gelatin capsules with a white opaque colored cap imprinted with a Glenmark logo 'G' in black ink and a white opaque colored body imprinted with '584' in black ink. They are supplied as follows:

NDC 68462-584-76 Carton of 6 capsules (containing 1 x 6 unit-dose blisters)
NDC 68462-584-58 Blister card of 2 capsules (2-day pack containing two 80 mg capsules)

Aprepitant Capsules USP, 3-day pack (125 mg/80 mg/80 mg):

NDC 68462-112-33 Blister card of 3 capsules (3-day pack containing one 125 mg capsule and two 80 mg capsules)

Aprepitant Capsules USP, 40 mg: hard gelatin capsules with a mustard yellow colored cap imprinted with a Glenmark logo 'G' in black ink and a white opaque colored body imprinted with '583' in black ink. They are supplied as follows:

NDC 68462-583-11 Carton of 10 capsules (containing 1 x 10 unit-dose blisters)
NDC 68462-583-85 Carton of 5 capsules (containing 5 x 1 unit-dose blisters)
NDC 68462-583-40 Carton of 1 capsule (containing 1 unit-dose blisters)

Storage and Handling

Store at 20°C to 25°C (68°F to 77°F); excursions permitted to 15°C to 30°C (59°F to 86°F) [see USP Controlled Room Temperature].

17 PATIENT COUNSELING INFORMATION

Advise the patient to read the FDA-approved patient labeling (Patient Information).

Hypersensitivity Reactions

Advise patients that hypersensitivity reactions, including anaphylaxis, have been reported in patients taking aprepitant. Advise patients to stop taking aprepitant and seek immediate medical attention if they experience signs or symptoms of a hypersensitivity reaction, such as hives, rash and itching, skin peeling or sores, or difficulty in breathing or swallowing.

Drug Interactions

Advise patients to discuss all medications they are taking, including other prescription, non-prescription medication or herbal products [see Contraindications (4), Warnings and Precautions (5.1)].

Warfarin: Instruct patients on chronic warfarin therapy to follow instructions from their healthcare provider regarding blood draws to monitor their INR during the 2-week period, particularly at 7 to 10 days, following initiation of the 3-day regimen of aprepitant with each chemotherapy cycle, or following administration of a single 40-mg dose of aprepitant for the prevention of postoperative nausea and vomiting [see Warnings and Precautions (5.2)].

Hormonal Contraceptives: Advise patients that administration of aprepitant may reduce the efficacy of hormonal contraceptives. Instruct patients to use effective alternative or back-up methods of contraception (such as condoms and spermicides) during treatment with aprepitant and for 1 month following the last dose of aprepitant [see Warnings and Precautions (5.3), Use in Specific Populations (8.3)].

Distributed by:

Glenmark Pharmaceuticals Inc., USA

Elmwood Park, NJ 07407

Questions? 1 (888) 721-7115

www.glenmarkpharma-us.com

July 2025

Patient Information

Aprepitant (a-PRE-pi-tant)

Capsules

Read this Patient Information before you start taking aprepitant capsules and each time you get a refill. There may be new information. This information does not take the place of talking with your healthcare provider about your medical condition or treatment.

What are aprepitant capsules?

Aprepitant capsules are a prescription medicine used:

- with other medicines that treat nausea and vomiting in patients 12 years of age and older to prevent nausea and vomiting caused by certain anti-cancer (chemotherapy) medicines
- In adults to prevent nausea and vomiting after surgery

Aprepitant capsules are not used to treat nausea and vomiting that you already have.

Aprepitant capsules should not be used continuously for a long time (chronic use).

Who should not take aprepitant capsules?

Do not take aprepitant capsules if you:

- are allergic to aprepitant or any of the ingredients in aprepitant capsules. See the end of this leaflet for a complete list of ingredients in aprepitant capsules.
- are taking pimozide (ORAP®)

What should I tell my healthcare provider before taking aprepitant capsules?

Before you take aprepitant capsules, tell your healthcare provider if you:

- have liver problems
- are pregnant or plan to become pregnant. It is not known if aprepitant capsules can harm your unborn baby.
  - Women who use birth control medicines containing hormones to prevent pregnancy (birth control pills, skin patches, implants, and certain IUDs) should also use a back-up method of birth control that does not contain hormones, such as condoms and spermicides, during treatment with aprepitant capsules and for 1 month after your last dose of aprepitant capsules.
- are breastfeeding or plan to breastfeed. It is not known if aprepitant passes into your breast milk. Talk to your healthcare provider about the best way to feed your baby if you take aprepitant capsules.

Tell your healthcare provider about all the medicines you take, including prescription and over-the-counter medicines, vitamins, and herbal supplements.

Aprepitant capsules may affect the way other medicines work, and other medicines may affect how aprepitant capsules work causing serious side effects.

Know the medicines you take. Keep a list of them to show your healthcare provider or pharmacist when you get a new medicine.

How should I take aprepitant capsules?

- Take aprepitant capsules exactly as prescribed.
- Swallow aprepitant capsules whole.
- Aprepitant capsules may be taken with or without food.
- If you take too much aprepitant, call your healthcare provider, or go to the nearest hospital emergency room.
- Aprepitant capsules are taken as 3 doses over 3 days - starting on the day you have chemotherapy, and for the following 2 days.
- In adults, your healthcare provider may prescribe aprepitant capsules for you:
Capsules of aprepitant by mouth for all 3 doses:
- You should get a package that has 3 capsules of aprepitant.
- Day 1 (Day of chemotherapy): Take one 125 mg capsule of aprepitant (white and pink) by mouth 1 hour before you start your chemotherapy treatment.
- Day 2 and Day 3: Take one 80 mg capsule of aprepitant (white) by mouth 1 hour before you start your chemotherapy treatment. If no chemotherapy treatment is given on Days 2 and 3, aprepitant capsules should be taken in the morning.
- In children 12 years of age and older who can swallow capsules by mouth, aprepitant is prescribed as capsules of aprepitant by mouth for all 3 doses:
- You should get a package that has 3 capsules of aprepitant capsules.
- Day 1 (Day of chemotherapy): Take one 125 mg capsule of aprepitant capsules (white and pink) by mouth 1 hour before you start your chemotherapy treatment.
- Day 2 and Day 3: Take one 80 mg capsule of aprepitant (white) by mouth 1 hour before you start your chemotherapy treatment. If no chemotherapy treatment is given on Days 2 and 3, aprepitant should be taken in the morning.
- If you are an adult and are having surgery:
- Your doctor will prescribe a 40 mg capsule of aprepitant for you before surgery. Take aprepitant within 3 hours before surgery.
- Follow your healthcare provider’s instructions about restrictions on eating and drinking before surgery.
- If you take the blood thinner medicine warfarin sodium (COUMADIN®, JANTOVEN®), your healthcare provider may do blood tests after you take aprepitant capsules to check your blood clotting.

What are the possible side effects of aprepitant capsules?

- In adults taking aprepitant capsules to prevent nausea and vomiting caused by chemotherapy, the most common side effects include tiredness, diarrhea, weakness, indigestion, stomach (abdominal) pain, hiccups, decrease in white blood cell count, dehydration, and changes in liver function tests.
- In adults taking aprepitant capsules to prevent nausea and vomiting after surgery, the most common side effects include constipation and low blood pressure (hypotension).
- In children 6 months to 17 years of age, the most common side effects include decrease in white blood cell count, headache, diarrhea, decreased appetite, cough, tiredness, decrease in red blood cell count, dizziness, and hiccups.

Tell your healthcare provider if you have any side effect that bothers you or that does not go away. These are not all of the possible side effects of aprepitant capsules. For more information ask your healthcare provider or pharmacist.

Call your healthcare provider for medical advice about side effects. You may report side effects to FDA at 1-800-FDA-1088.

How should I store aprepitant capsules?

- Store at room temperature, between 68°F to 77°F (20°C to 25°C).

Keep aprepitant capsules and all medicines out of the reach of children.

General information about the safe and effective use of aprepitant capsules

Medicines are sometimes prescribed for purposes other than those listed in a Patient Information leaflet. Do not use aprepitant capsules for a condition for which they were not prescribed. Do not give aprepitant capsules to other people, even if they have the same symptoms you have. They may harm them. You can ask your healthcare provider or pharmacist for information about aprepitant capsules that is written for health professionals. For more information about aprepitant capsules call 1 (888) 721-7115.

What are the ingredients in aprepitant capsules?

Active ingredient: aprepitant

Inactive ingredients: colloidal silicon dioxide, hydroxyethyl cellulose, microcrystalline cellulose, mannitol, poloxamer, povidone, sodium stearyl fumarate, vitamin E polyethylene glycol succinate, and purified water. The capsule shell excipients are gelatin, sodium lauryl sulphate and titanium dioxide. The 40-mg capsule shell also contains iron oxide yellow, and the 125-mg capsule also contains FD&C Red #3. Non-volatile solvents in the imprinting ink are shellac, iron oxide black and potassium hydroxide.

All trademarks are the property of their respective owners.

Distributed by:

Glenmark Pharmaceuticals Inc., USA

Elmwood Park, NJ 07407

Questions? 1 (888) 721-7115

www.glenmarkpharma-us.com

This Patient Information has been approved by the U.S. Food and Drug Administration.

Revised: July 2025